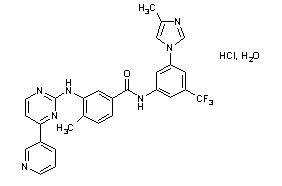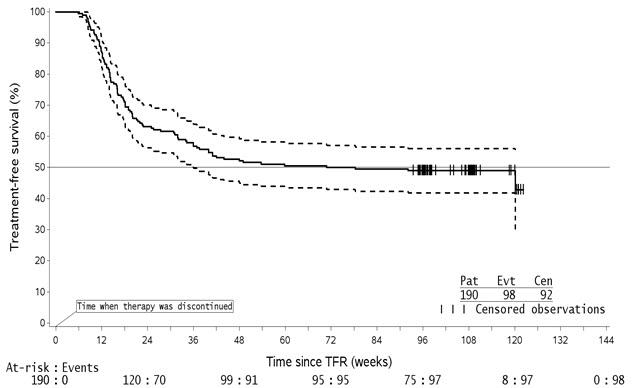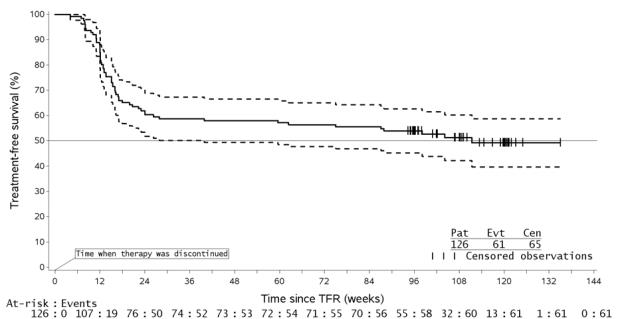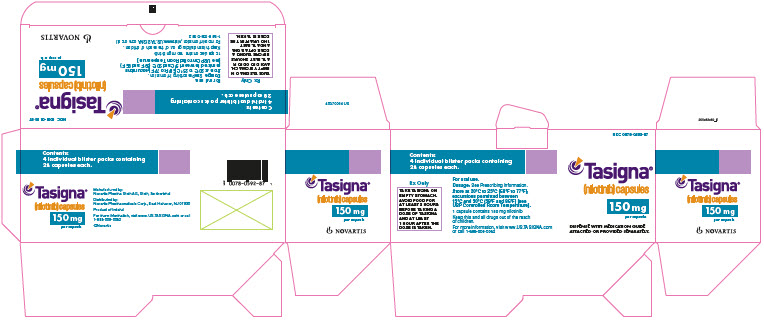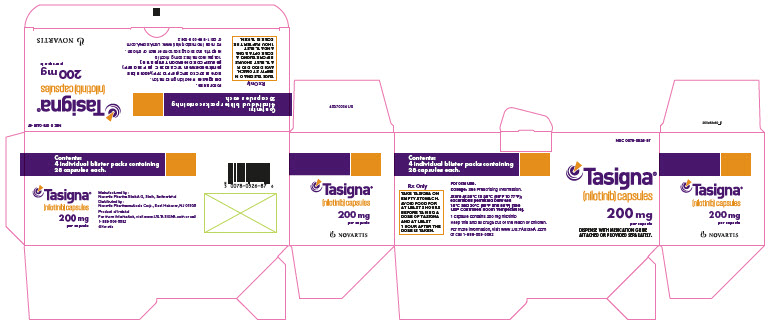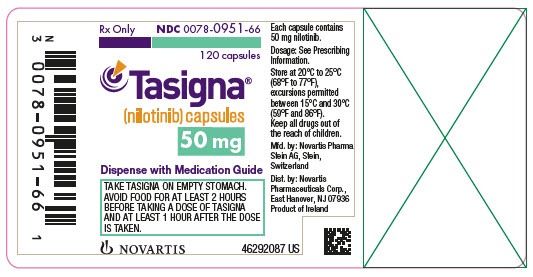 DRUG LABEL: Tasigna
NDC: 0078-0526 | Form: CAPSULE
Manufacturer: Novartis Pharmaceuticals Corporation
Category: prescription | Type: HUMAN PRESCRIPTION DRUG LABEL
Date: 20251216

ACTIVE INGREDIENTS: NILOTINIB HYDROCHLORIDE MONOHYDRATE 200 mg/1 1
INACTIVE INGREDIENTS: SILICON DIOXIDE; CROSPOVIDONE; LACTOSE MONOHYDRATE; MAGNESIUM STEARATE; POLOXAMER 188; GELATIN; FERRIC OXIDE RED; FERRIC OXIDE YELLOW; TITANIUM DIOXIDE

HIGHLIGHTS OF PRESCRIBING INFORMATION

These highlights do not include all the information needed to use TASIGNA safely and effectively. See full prescribing information for TASIGNA.
TASIGNA® (nilotinib) capsules, for oral use
Initial U.S. Approval: 2007

WARNING: QT PROLONGATION and SUDDEN DEATHS

See full prescribing information for complete boxed warning.

- Tasigna prolongs the QT interval. Prior to Tasigna administration and periodically, monitor for hypokalemia or hypomagnesemia and correct deficiencies. (5.2) Obtain ECGs to monitor the QTc at baseline, seven days after initiation, and periodically thereafter, and following any dose adjustments. (5.2, 5.3, 5.7, 5.12)
- Sudden deaths have been reported in patients receiving Tasigna. (5.3) Do not administer Tasigna to patients with hypokalemia, hypomagnesemia, or long QT syndrome. (4, 5.2)
- Avoid use of concomitant drugs known to prolong the QT interval and strong CYP3A4 inhibitors. (7.1, 7.2)
- Avoid food 2 hours before and 1 hour after taking the dose. (2.1)

1 INDICATIONS AND USAGE

Tasigna is a kinase inhibitor indicated for the treatment of:

- Adult and pediatric patients greater than or equal to 1 year of age with newly diagnosed Philadelphia chromosome positive chronic myeloid leukemia (Ph+ CML) in chronic phase. (1.1)
- Adult patients with chronic phase (CP) and accelerated phase (AP) Ph+ CML resistant to or intolerant to prior therapy that included imatinib. (1.2)
- Pediatric patients greater than or equal to 1 year of age with Ph+ CML-CP and CML-AP resistant or intolerant to prior tyrosine-kinase inhibitor (TKI) therapy. (1.3)

2 DOSAGE AND ADMINISTRATION

- Recommended Adult Dose: Newly diagnosed Ph+ CML-CP: 300 mg orally twice daily. Resistant or intolerant Ph+ CML-CP and CML-AP: 400 mg orally twice daily. (2.1)
- Recommended Pediatric Dose: Newly Diagnosed Ph+ CML-CP or Ph+ CML-CP and CML-AP resistant or intolerant to prior TKI therapy: 230 mg/m^2 orally twice daily, rounded to the nearest 50 mg dose (to a maximum single dose of 400 mg). (2.1)
- See Dosage and Administration for full dosing instructions and dose-reduction instructions for toxicity. (2.1)
- Reduce starting dose in patients with baseline hepatic impairment. (2.7)
- Eligible newly diagnosed adult patients with Ph+ CML-CP who have received Tasigna for a minimum of 3 years and have achieved a sustained molecular response (MR4.5) and patients with Ph+ CML-CP resistant or intolerant to imatinib who have received Tasigna for at least 3 years and have achieved a sustained molecular response (MR4.5) may be considered for treatment discontinuation. (2.2, 2.3, 5.16)

3 DOSAGE FORMS AND STRENGTHS

Capsules: 50 mg, 150 mg, and 200 mg (3)

4 CONTRAINDICATIONS

Tasigna is contraindicated in patients with hypokalemia, hypomagnesemia, or long QT syndrome. (4)

5 WARNINGS AND PRECAUTIONS

- Myelosuppression: Monitor complete blood count (CBC) during therapy and manage by treatment interruption or dose reduction. (5.1)
- Cardiac and Arterial Vascular Occlusive Events: Evaluate cardiovascular status, monitor and manage cardiovascular risk factors during Tasigna therapy. (5.4)
- Pancreatitis and Elevated Serum Lipase: Monitor serum lipase; if elevations are accompanied by abdominal symptoms, interrupt doses and consider appropriate diagnostics to exclude pancreatitis. (5.5)
- Hepatotoxicity: Monitor hepatic function tests monthly or as clinically indicated. (5.6)
- Electrolyte Abnormalities: Tasigna can cause hypophosphatemia, hypokalemia, hyperkalemia, hypocalcemia, and hyponatremia. Correct electrolyte abnormalities prior to initiating Tasigna and monitor periodically during therapy. (5.7)
- Tumor Lysis Syndrome: Maintain adequate hydration and correct uric acid levels prior to initiating therapy with Tasigna. (5.8)
- Hemorrhage: Hemorrhage from any site may occur. Advise patients to report signs and symptoms of bleeding and medically manage as needed. (5.9)
- Fluid Retention: Monitor patients for unexpected rapid weight gain, swelling, and shortness of breath. Manage medically. (5.13)
- Effects on Growth and Development in Pediatric Patients: Growth retardation has been reported in pediatric patients treated with Tasigna. Monitor growth and development in pediatric patients. (5.14)
- Embryo-Fetal Toxicity: Advise females of reproductive potential of potential risk to a fetus and to use effective contraception. (5.15, 8.1, 8.3)
- Treatment Discontinuation: Patients must have typical BCR-ABL transcripts. An FDA-authorized test with a detection limit below MR4.5 must be used to determine eligibility for discontinuation. Patients must be frequently monitored by the FDA authorized test to detect possible loss of remission. (5.16)

6 ADVERSE REACTIONS

The most commonly reported non-hematologic adverse reactions (≥ 20%) in adult and pediatric patients were nausea, rash, headache, fatigue, pruritus, vomiting, diarrhea, cough, constipation, arthralgia, nasopharyngitis, pyrexia, and night sweats. Hematologic adverse drug reactions include myelosuppression: thrombocytopenia, neutropenia, and anemia. (6.1)

To report SUSPECTED ADVERSE REACTIONS, contact Novartis Pharmaceuticals Corporation at 1-888-669-6682 or FDA at 1-800-FDA-1088 or www.fda.gov/medwatch.

7 DRUG INTERACTIONS

- Strong CYP3A Inhibitors: Avoid concomitant use with Tasigna, or reduce Tasigna dose if coadministration cannot be avoided. (7.1)
- Strong CYP3A Inducers: Avoid concomitant use with Tasigna. (7.1)
- Proton Pump Inhibitors: Use short-acting antacids or H2 blockers as an alternative to proton pump inhibitors. (7.1)

8 USE IN SPECIFIC POPULATIONS

- Lactation: Advise women not to breastfeed. (8.2)

FULL PRESCRIBING INFORMATION

WARNING: QT PROLONGATION and SUDDEN DEATHS

- Tasigna prolongs the QT interval. Prior to Tasigna administration and periodically, monitor for hypokalemia or hypomagnesemia and correct deficiencies [see Warnings and Precautions (5.2)]. Obtain ECGs to monitor the QTc at baseline, seven days after initiation, and periodically thereafter, and following any dose adjustments [see Warnings and Precautions (5.2, 5.3, 5.7, 5.12)].
- Sudden deaths have been reported in patients receiving Tasigna [see Warnings and Precautions (5.3)]. Do not administer Tasigna to patients with hypokalemia, hypomagnesemia, or long QT syndrome [see Contraindications (4), Warnings and Precautions (5.2)].
- Avoid use of concomitant drugs known to prolong the QT interval and strong CYP3A4 inhibitors [see Drug Interactions (7.1, 7.2)].
- Avoid food 2 hours before and 1 hour after taking the dose [see Dosage and Administration (2.1)].

1 INDICATIONS AND USAGE

1.1 Adult and Pediatric Patients With Newly Diagnosed Ph+ CML-CP

Tasigna is indicated for the treatment of adult and pediatric patients greater than or equal to 1 year of age with newly diagnosed Philadelphia chromosome positive chronic myeloid leukemia (Ph+ CML) in chronic phase.

1.2 Adult Patients With Resistant or Intolerant Ph+ CML-CP and CML-AP

Tasigna is indicated for the treatment of adult patients with chronic phase and accelerated phase Philadelphia chromosome positive chronic myelogenous leukemia (Ph+ CML) resistant or intolerant to prior therapy that included imatinib.

1.3 Pediatric Patients With Resistant or Intolerant Ph+ CML-CP and CML-AP

Tasigna is indicated for the treatment of pediatric patients greater than or equal to 1 year of age with chronic phase and accelerated phase Philadelphia chromosome positive chronic myeloid leukemia (Ph+ CML) with resistance or intolerance to prior tyrosine-kinase inhibitor (TKI) therapy.

2 DOSAGE AND ADMINISTRATION

2.1 Recommended Dosage

Dose Tasigna twice daily at approximately 12-hour intervals on an empty stomach. No food should be consumed for at least 2 hours before the dose is taken and for at least 1 hour after the dose is taken. Advise patients to swallow the capsules whole with water [see Boxed Warning, Clinical Pharmacology (12.3)].

For patients who are unable to swallow capsules, the contents of each capsule may be dispersed in 1 teaspoon of applesauce (puréed apple). The mixture should be taken immediately (within 15 minutes) and should not be stored for future use [see Clinical Pharmacology (12.3)].

Tasigna may be given in combination with hematopoietic growth factors, such as erythropoietin or G-CSF if clinically indicated. Tasigna may be given with hydroxyurea or anagrelide if clinically indicated.

Dosage in Adult Patients with Newly Diagnosed Ph+ CML-CP

The recommended dosage of Tasigna is 300 mg orally twice daily.

Dosage in Adult Patients with Resistant or Intolerant Ph+ CML-CP and CML-AP

The recommended dosage of Tasigna is 400 mg orally twice daily.

Dosage in Pediatric Patients with Newly Diagnosed Ph+ CML-CP or Resistant or Intolerant Ph+ CML-CP and CML-AP

The recommended dosage of Tasigna for pediatric patients is 230 mg/m^2 orally twice daily, rounded to the nearest 50 mg dose (to a maximum single dose of 400 mg) (see Table 1). If needed, attain the desired dose by combining different strengths of Tasigna capsules. Continue treatment as long as clinical benefit is observed or until unacceptable toxicity occurs.

Table 1: Pediatric Dosing of Tasigna (230 mg/m^2 Twice Daily, Maximum Single Dose of 400 mg)
Body surface area | Single dose | Total daily dose
Up to 0.32 m^2 | 50 mg | 100 mg
0.33 – 0.54 m^2 | 100 mg | 200 mg
0.55 – 0.76 m^2 | 150 mg | 300 mg
0.77 – 0.97 m^2 | 200 mg | 400 mg
0.98 – 1.19 m^2 | 250 mg | 500 mg
1.20 – 1.41 m^2 | 300 mg | 600 mg
1.42 – 1.63 m^2 | 350 mg | 700 mg
≥ 1.64 m^2 | 400 mg | 800 mg

2.2 Discontinuation of Treatment After a Sustained Molecular Response (MR4.5) on Tasigna

Patient Selection

Eligibility for Discontinuation of Treatment

Ph+ CML-CP patients with typical BCR-ABL transcripts, who have been taking Tasigna for a minimum of 3 years and have achieved a sustained molecular response (MR4.5, corresponding to = BCR-ABL/ABL ≤ 0.0032% IS), may be eligible for treatment discontinuation [see Clinical Studies (14.3, 14.4)]. Information on FDA authorized tests for the detection and quantitation of BCR-ABL transcripts to determine eligibility for treatment discontinuation is available at http://www.fda.gov/CompanionDiagnostics.

Patients with typical BCR-ABL transcripts (e13a2/b2a2 or e14a2/b3a2), who achieve the sustained MR4.5 criteria, are eligible for discontinuation of Tasigna. Patients must continue to be monitored for possible loss of molecular remission after treatment discontinuation. Use the same FDA-authorized test to consistently monitor molecular response levels while on and off treatment.

Consider discontinuation in patients with newly diagnosed Ph+ CML-CP who have:

- been treated with Tasigna for at least 3 years
- maintained a molecular response of at least MR4.0 (corresponding to = BCR-ABL/ABL ≤ 0.01% IS) for one year prior to discontinuation of therapy
- achieved an MR4.5 for the last assessment taken immediately prior to discontinuation of therapy
- been confirmed to express the typical BCR-ABL transcripts (e13a2/b2a2 or e14a2/b3a2)
- no history of accelerated phase or blast crisis
- no history of prior attempts of treatment-free remission discontinuation that resulted in relapse.

Consider discontinuation in patients with Ph+ CML-CP that are resistant or intolerant to imatinib who have achieved a sustained molecular response (MR4.5) on Tasigna who have:

- been treated with Tasigna for a minimum of 3 years
- been treated with imatinib only prior to treatment with Tasigna
- achieved a molecular response of MR4.5 (corresponding to = BCR-ABL/ABL ≤ 0.0032% IS)
- sustained an MR4.5 for a minimum of one year immediately prior to discontinuation of therapy
- been confirmed to express the typical BCR-ABL transcripts (e13a2/b2a2 or e14a2/b3a2)
- no history of accelerated phase or blast crisis
- no history of prior attempts of treatment-free remission discontinuation that resulted in relapse.

Monitor BCR-ABL transcript levels and complete blood count (CBC) with differential in patients who have discontinued Tasigna therapy monthly for one year, then every 6 weeks for the second year, and every 12 weeks thereafter [see Warnings and Precautions (5.16)].

Upon the loss of MR4.0 (corresponding to = BCR-ABL/ABL ≤ 0.01% IS) during the treatment-free phase, monitor BCR-ABL transcript levels every 2 weeks until BCR-ABL levels remain lower than major molecular response [(MMR), corresponding to MR3.0 or = BCR-ABL/ABL ≤ 0.1% IS] for 4 consecutive measurements. The patient can then proceed to the original monitoring schedule.

2.3 Reinitiation of Treatment in Patients Who Lose Molecular Response After Discontinuation of Therapy With Tasigna

- Newly diagnosed patients who lose MMR must reinitiate treatment within 4 weeks at the dose level prior to discontinuation of therapy [see Warnings and Precautions (5.16)]. Patients who reinitiate Tasigna therapy should have their BCR-ABL transcript levels monitored monthly until major molecular response is re-established and every 12 weeks thereafter.
- Patients resistant or intolerant to prior treatment that included imatinib with confirmed loss of MR4.0 (2 consecutive measures separated by at least 4 weeks showing loss of MR4.0) or loss of MMR must reinitiate treatment within 4 weeks at the dose level prior to discontinuation of therapy [see Warnings and Precautions (5.16)]. Patients who reinitiate Tasigna therapy should have their BCR-ABL transcript levels monitored monthly until previous major molecular response or MR4.0 is re-established and every 12 weeks thereafter.

2.4 Dosage Modification for QT Interval Prolongation

See Table 2 for dose adjustments for QT interval prolongation [see Warnings and Precautions (5.2), Clinical Pharmacology (12.2)].

Table 2: Dosage Adjustments for Adult and Pediatric Patients With QT Prolongation
Degree of QTc prolongation | Dosage adjustment
ECGs with a QTc greater than 480 msec | 1. Withhold Tasigna, and perform an analysis of serum potassium and magnesium, and if below lower limit of normal, correct with supplements to within normal limits. Concomitant medication usage must be reviewed. 2. Resume within 2 weeks at prior dose if QTcF returns to less than 450 msec and to within 20 msec of baseline. 3. If QTcF is between 450 msec and 480 msec after 2 weeks, reduce the dose to 400 mg once daily in adults and 230 mg/m^2 once daily in pediatric patients. 4. Discontinue Tasigna if, following dose-reduction to 400 mg once daily in adults and 230 mg/m^2 once daily in pediatric patients, QTcF returns to greater than 480 msec. 5. An ECG should be repeated approximately 7 days after any dose adjustment.
Abbreviation: ECG, electrocardiogram.

2.5 Dosage Modifications for Myelosuppression

Withhold or reduce Tasigna dosage for hematological toxicities (neutropenia, thrombocytopenia) that are not related to underlying leukemia (Table 3) [see Warnings and Precautions (5.1)].

Table 3: Dosage Adjustments for Neutropenia and Thrombocytopenia
Diagnosis | Degree of myelosuppression | Dosage adjustment
Adult patients with:; - Newly diagnosed Ph+ CML in chronic phase at 300 mg twice daily - Resistant or intolerant Ph+ CML in chronic phase or accelerated phase at 400 mg twice daily | ANC less than 1.0 x 10^9/L and/or platelet counts less than 50 x 10^9/L | 1. Stop Tasigna, and monitor blood counts. 2. Resume within 2 weeks at prior dose if ANC greater than 1.0 x 10^9/L and platelets greater than 50 x 10^9/L. 3. If blood counts remain low for greater than 2 weeks, reduce the dose to 400 mg once daily.
Pediatric patients with:; - Newly diagnosed Ph+ CML in chronic phase at 230 mg/m^2 twice daily - Resistant or intolerant Ph+ CML in chronic phase at 230 mg/m^2 twice daily | ANC less than 1.0 x 10^9/L and/or platelet counts less than 50 x 10^9/L | 1. Stop Tasigna and monitor blood counts. 2. Resume within 2 weeks at prior dose if ANC greater than 1.5 x 10^9/L and/or platelets greater than 75 x 10^9/L. 3. If blood counts remain low for greater than 2 weeks, a dose reduction to 230 mg/m^2 once daily may be required. 4. If event occurs after dose reduction, consider discontinuing treatment.
Abbreviations: ANC, absolute neutrophil count; Ph+ CML, Philadelphia chromosome positive chronic myeloid leukemia.

2.6 Dosage Modifications for Selected Non-Hematologic Laboratory Abnormalities and Other Toxicities

See Table 4 for dosage adjustments for elevations of lipase, amylase, bilirubin, and/or hepatic transaminases [see Warnings and Precautions (5.5, 5.6), Adverse Reactions (6.1)].

Table 4: Dosage Adjustments for Selected Non-Hematologic Laboratory Abnormalities
Degree of non-hematologic laboratory abnormality | Dosage adjustment
Elevated serum lipase or amylase greater than or equal to Grade 3 | Adult patients: 1. Withhold Tasigna, and monitor serum lipase or amylase. 2. Resume treatment at 400 mg once daily if serum lipase or amylase returns to less than or equal to Grade 1.
 | Pediatric patients: 1. Interrupt Tasigna until the event returns to less than or equal to Grade 1. 2. Resume treatment at 230 mg/m^2 once daily if prior dose was 230 mg/m^2 twice daily; discontinue treatment if prior dose was 230 mg/m^2 once daily.
Elevated bilirubin greater than or equal to Grade 3 in adult patients and greater than or equal to Grade 2 in pediatric patients | Adult patients: 1. Withhold Tasigna, and monitor bilirubin. 2. Resume treatment at 400 mg once daily if bilirubin returns to less than or equal to Grade 1.
Elevated bilirubin greater than or equal to Grade 3 in adult patients and greater than or equal to Grade 2 in pediatric patients | Pediatric patients: 1. Interrupt Tasigna until the event returns to less than or equal to Grade 1. 2. Resume treatment at 230 mg/m^2 once daily if prior dose was 230 mg/m^2 twice daily; discontinue treatment if prior dose was 230 mg/m^2 once daily, and recovery to less than or equal to Grade 1 takes longer than 28 days.
Elevated hepatic transaminases greater than or equal to Grade 3 | Adult patients: 1. Withhold Tasigna, and monitor hepatic transaminases. 2. Resume treatment at 400 mg once daily if hepatic transaminases returns to less than or equal to Grade 1.
 | Pediatric patients: 1. Interrupt Tasigna until the event returns to less than or equal to Grade 1. 2. Resume treatment at 230 mg/m^2 once daily if prior dose was 230 mg/m^2 twice daily; discontinue treatment if prior dose was 230 mg/m^2 once daily, and recovery to less than or equal to Grade 1 takes longer than 28 days.

If clinically significant moderate or severe non-hematologic toxicity develops (including medically severe fluid retention), see Table 5 for dosage adjustments [see Adverse Reactions (6.1)].

Table 5: Dosage Adjustments for Other Non-Hematologic Toxicities
Degree of “other Non-hematologic toxicity” | Dosage adjustment
Other clinically moderate or severe non-hematologic toxicity | Adult patients: 1. Withhold Tasigna until toxicity has resolved. 2. Resume treatment at 400 mg once daily if previous dose was 300 mg twice daily in adult patients newly diagnosed with CML-CP or 400 mg twice daily in adult patients with resistant or intolerant CML-CP and CML-AP. 3. Discontinue treatment if the prior dose was 400 mg once daily in adult patients. 4. If clinically appropriate, consider re-escalation of the dose to 300 mg (newly diagnosed Ph+ CML-CP) or 400 mg (resistant or intolerant Ph+ CML-CP and CML-AP) twice daily.
 | Pediatric patients: 1. Interrupt Tasigna until toxicity has resolved. 2. Resume treatment at 230 mg/m^2 once daily if previous dose was 230 mg/m^2 twice daily; discontinue treatment if prior dose was 230 mg/m^2 once daily. 3. If clinically appropriate, consider re-escalation of the dose to 230 mg/m^2 twice daily.
Abbreviations: CML-AP, chronic myeloid leukemia-accelerated phase; CML-CP, chronic myeloid leukemia-chronic phase; Ph+, Philadelphia chromosome positive.

2.7 Dosage Modification for Hepatic Impairment

If possible, consider alternative therapies. If Tasigna must be administered to patients with hepatic impairment, consider the following dose reduction [see Use in Specific Populations (8.7)]:

Table 6: Dose Adjustments for Adult Patients With Hepatic Impairment
Diagnosis | Degree of hepatic impairment | Dosage adjustment
Newly diagnosed Ph+ CML in chronic phase | Mild (Child-Pugh A), Moderate (Child-Pugh B), or Severe (Child-Pugh C) | Reduce dosage to 200 mg twice daily. Increase dosage to 300 mg twice daily based on tolerability.
Resistant or intolerant Ph+ CML in chronic phase or accelerated phase | Mild or Moderate | Reduce dosage to 300 mg twice daily. Increase dosage to 400 mg twice daily based on tolerability.
 | Severe | Reduce dosage to 200 mg twice daily. Increase dosage to 300 mg twice daily and then to 400 mg twice daily based on tolerability.

2.8 Dosage Modification With Concomitant Strong CYP3A4 Inhibitors

Avoid the concomitant use of strong CYP3A4 inhibitors. Should treatment with any of these agents be required, interrupt therapy with Tasigna. If patients must be coadministered a strong CYP3A4 inhibitor, reduce dosage to 300 mg once daily in patients with resistant or intolerant Ph+ CML or to 200 mg once daily in patients with newly diagnosed Ph+ CML-CP. However, there are no clinical data with this dose adjustment in patients receiving strong CYP3A4 inhibitors. If the strong inhibitor is discontinued, allow a washout period before adjusting Tasigna dose upward to the indicated dose. For patients who cannot avoid use of strong CYP3A4 inhibitors, monitor closely for prolongation of the QT interval [see Boxed Warning, Warnings and Precautions (5.2), Drug Interactions (7.1, 7.2), Clinical Pharmacology (12.3)].

3 DOSAGE FORMS AND STRENGTHS

Capsules:

- 50 mg red opaque cap and light-yellow opaque body hard gelatin capsules with black radial imprint “NVR/ABL.”
- 150 mg red opaque hard gelatin capsules with black axial imprint “NVR/BCR.”
- 200 mg light-yellow opaque hard gelatin capsules with a red axial imprint “NVR/TKI.”

4 CONTRAINDICATIONS

Tasigna is contraindicated in patients with hypokalemia, hypomagnesemia, or long QT syndrome [see Boxed Warning].

5 WARNINGS AND PRECAUTIONS

5.1 Myelosuppression

Treatment with Tasigna can cause Grade 3/4 thrombocytopenia, neutropenia, and anemia. Perform CBCs every 2 weeks for the first 2 months and then monthly thereafter, or as clinically indicated. Myelosuppression was generally reversible and usually managed by withholding Tasigna temporarily or dose reduction [see Dosage and Administration (2.5)].

5.2 QT Prolongation

Tasigna has been shown to prolong cardiac ventricular repolarization as measured by the QT interval on the surface electrocardiogram (ECG) in a concentration-dependent manner [see Adverse Reactions (6.1), Clinical Pharmacology (12.2)]. Prolongation of the QT interval can result in a type of ventricular tachycardia called torsade de pointes, which may result in syncope, seizure, and/or death. Electrocardiograms should be performed at baseline, 7 days after initiation of Tasigna, and periodically as clinically indicated and following dose adjustments [see Dosage and Administration (2.4), Warnings and Precautions (5.12)].

Tasigna should not be used in patients who have hypokalemia, hypomagnesemia, or long QT syndrome. Before initiating Tasigna and periodically, test electrolyte, calcium, and magnesium blood levels. Hypokalemia or hypomagnesemia must be corrected prior to initiating Tasigna and these electrolytes should be monitored periodically during therapy [see Warnings and Precautions (5.12)].

Significant prolongation of the QT interval may occur when Tasigna is inappropriately taken with food and/or strong CYP3A4 inhibitors and/or medicinal products with a known potential to prolong QT. Therefore, coadministration with food must be avoided and concomitant use with strong CYP3A4 inhibitors and/or medicinal products with a known potential to prolong QT should be avoided [see Dosage and Administration (2.1), Drug Interactions (7.1, 7.2)]. The presence of hypokalemia and hypomagnesemia may further prolong the QT interval [see Warnings and Precautions (5.7, 5.12)].

5.3 Sudden Deaths

Sudden deaths have been reported in 0.3% of patients with CML treated with Tasigna in clinical studies of 5661 patients. The relative early occurrence of some of these deaths relative to the initiation of Tasigna suggests the possibility that ventricular repolarization abnormalities may have contributed to their occurrence.

5.4 Cardiac and Arterial Vascular Occlusive Events

Cardiovascular events, including arterial vascular occlusive events, were reported in a randomized, clinical trial in newly diagnosed CML patients and observed in the postmarketing reports of patients receiving Tasigna therapy [see Adverse Reactions (6.1)]. With a median time on therapy of 60 months in the clinical trial, cardiovascular events, including arterial vascular occlusive events, occurred in 9% and 15% of patients in the Tasigna 300 and 400 mg twice daily arms, respectively, and in 3.2% in the imatinib arm. These included cases of cardiovascular events, including ischemic heart disease-related cardiac events (5% and 9% in the Tasigna 300 mg and 400 mg twice daily arms, respectively, and 2.5% in the imatinib arm), peripheral arterial occlusive disease (3.6% and 2.9% in the Tasigna 300 mg and 400 mg twice daily arms, respectively, and 0% in the imatinib arm), and ischemic cerebrovascular events (1.4% and 3.2% in the Tasigna 300 mg and 400 mg twice daily arms, respectively, and 0.7% in the imatinib arm). If acute signs or symptoms of cardiovascular events occur, advise patients to seek immediate medical attention. The cardiovascular status of patients should be evaluated and cardiovascular risk factors should be monitored and actively managed during Tasigna therapy according to standard guidelines [see Dosage and Administration (2.4)].

5.5 Pancreatitis and Elevated Serum Lipase

Tasigna can cause increases in serum lipase [see Adverse Reactions (6.1)]. Patients with a previous history of pancreatitis may be at greater risk of elevated serum lipase. If lipase elevations are accompanied by abdominal symptoms, interrupt dosing and consider appropriate diagnostics to exclude pancreatitis [see Dosage and Administration (2.6)]. Test serum lipase levels monthly or as clinically indicated.

5.6 Hepatotoxicity

Tasigna may result in hepatotoxicity as measured by elevations in bilirubin, aspartate aminotransferase (AST), alanine aminotransferase (ALT), and alkaline phosphatase. Grade 3-4 elevations of bilirubin, AST, and ALT were reported at a higher frequency in pediatric than in adult patients. Monitor hepatic function tests monthly or as clinically indicated [see Warnings and Precautions (5.12)] and following dose adjustments. [see Dosage and Administration (2.6)].

5.7 Electrolyte Abnormalities

The use of Tasigna can cause hypophosphatemia, hypokalemia, hyperkalemia, hypocalcemia, and hyponatremia. Correct electrolyte abnormalities prior to initiating Tasigna and during therapy. Monitor these electrolytes periodically during therapy [see Warnings and Precautions (5.12)].

5.8 Tumor Lysis Syndrome

Tumor lysis syndrome (TLS) cases have been reported in Tasigna treated patients with resistant or intolerant CML. Malignant disease progression, high white blood cell (WBC) counts and/or dehydration were present in the majority of these cases. Due to potential for TLS, maintain adequate hydration and correct uric acid levels prior to initiating therapy with Tasigna.

5.9 Hemorrhage

Serious hemorrhagic events, including fatal events, have occurred in patients with CML treated with Tasigna. In a randomized trial in patients with newly diagnosed Ph+ CML in chronic phase comparing Tasigna and imatinib, Grade 3 or 4 hemorrhage occurred in 1.1% of patients in the Tasigna 300 mg twice daily arm, in 1.8% of patients in the Tasigna 400 mg twice daily arm, and 0.4% of patients in the imatinib arm. GI hemorrhage occurred in 2.9% and 5% of patients in the Tasigna 300 mg twice daily and 400 mg twice daily arms and in 1.4% of patients in the imatinib arm, respectively. Grade 3 or 4 events occurred in 0.7% and 1.4% of patients in the Tasigna 300 mg twice daily and 400 mg twice daily arms, respectively, and in no patients in the imatinib arm. Monitor for signs and symptoms of bleeding and medically manage as needed.

5.10 Total Gastrectomy

Since the exposure of Tasigna is reduced in patients with total gastrectomy, perform more frequent monitoring of these patients. Consider dose increase or alternative therapy in patients with total gastrectomy [see Clinical Pharmacology (12.3)].

5.11 Lactose

Since the capsules contain lactose, Tasigna is not recommended for patients with rare hereditary problems of galactose intolerance, severe lactase deficiency with a severe degree of intolerance to lactose-containing products, or of glucose-galactose malabsorption.

5.12 Monitoring Laboratory Tests

Complete blood counts should be performed every 2 weeks for the first 2 months and then monthly thereafter. Perform chemistry panels, including electrolytes, calcium, magnesium, liver enzymes, lipid profile, and glucose prior to therapy and periodically. Electrocardiograms should be obtained at baseline, 7 days after initiation and periodically thereafter, as well as following dose adjustments [see Warnings and Precautions (5.2)]. Monitor lipid profiles and glucose periodically during the first year of Tasigna therapy and at least yearly during chronic therapy. Should treatment with any HMG-CoA reductase inhibitor (a lipid lowering agent) be needed to treat lipid elevations, evaluate the potential for a drug-drug interaction before initiating therapy as certain HMG-CoA reductase inhibitors are metabolized by the CYP3A4 pathway [see Drug Interactions (7.1)]. Assess glucose levels before initiating treatment with Tasigna and monitor during treatment as clinically indicated. If test results warrant therapy, physicians should follow their local standards of practice and treatment guidelines.

5.13 Fluid Retention

In the randomized trial in patients with newly diagnosed Ph+ CML in chronic phase, severe (Grade 3 or 4) fluid retention occurred in 3.9% and 2.9% of patients receiving Tasigna 300 mg twice daily and 400 mg twice daily, respectively, and in 2.5% of patients receiving imatinib. Effusions (including pleural effusion, pericardial effusion, ascites) or pulmonary edema, were observed in 2.2% and 1.1% of patients receiving Tasigna 300 mg twice daily and 400 mg twice daily, respectively, and in 2.1% of patients receiving imatinib. Effusions were severe (Grade 3 or 4) in 0.7% and 0.4% of patients receiving Tasigna 300 mg twice daily and 400 mg twice daily, respectively, and in no patients receiving imatinib. Similar events were also observed in postmarketing reports. Monitor patients for signs of severe fluid retention (e.g., unexpected rapid weight gain or swelling) and for symptoms of respiratory or cardiac compromise (e.g., shortness of breath) during Tasigna treatment; evaluate etiology and treat patients accordingly.

5.14 Effects on Growth and Development in Pediatric Patients

Growth retardation has been reported in pediatric patients with Ph+ CML in chronic phase treated with Tasigna. In a pediatric trial with 58 patients with Ph+ CML in chronic phase with a median exposure of 56.7 months, growth deceleration (crossing at least two main height percentile lines from baseline) was observed in eight patients: five (9%) crossed two main percentile lines from baseline and three (5%) crossed three main percentile lines from baseline (percentile lines: 5th, 10th, 25th, 50th, 75th, 90th, and 95th). Growth deceleration was more pronounced in children who were less than age 12 at baseline. Adverse reactions associated with growth retardation were reported in 3 patients (5%). Monitor growth and development in pediatric patients receiving Tasigna treatment.

5.15 Embryo-Fetal Toxicity

Based on findings from animal studies and its mechanism of action, Tasigna can cause fetal harm when administered to a pregnant woman. In animal reproduction studies, administration of nilotinib to pregnant rats and rabbits during organogenesis caused adverse developmental outcomes, including embryo-fetal lethality/fetal effects (small renal papilla, fetal edema, and skeletal variations) in rats and increased resorptions of fetuses and fetal skeletal variations in rabbits at maternal area under the curve (AUCs) approximately 2 and 0.5 times, respectively, the AUC in patients receiving the recommended dose. Advise pregnant women of the potential risk to a fetus.

Advise females of reproductive potential to use effective contraception during treatment and for 14 days after the last dose [see Use in Specific Populations (8.1, 8.3), Clinical Pharmacology (12.1)].

5.16 Monitoring of BCR-ABL Transcript Levels

Monitoring of BCR-ABL Transcript Levels in Patients Who Discontinued Tasigna

Monitor BCR-ABL transcript levels in patients eligible for treatment discontinuation using an FDA authorized test validated to measure molecular response levels with a sensitivity of at least MR4.5 (BCR-ABL/ABL ≤ 0.0032% IS). In patients who discontinue Tasigna therapy, assess BCR-ABL transcript levels monthly for one year, then every 6 weeks for the second year, and every 12 weeks thereafter during treatment discontinuation [see Clinical Studies (14.3,14.4), Dosage and Administration (2.2)].

Newly diagnosed patients must reinitiate Tasigna therapy within 4 weeks of a loss of major molecular response [(MMR), corresponding to MR3.0 or = BCR-ABL/ABL ≤ 0.1% IS].

Patients resistant or intolerant to prior treatment which included imatinib must reinitiate Tasigna therapy within 4 weeks of a loss of MMR or confirmed loss of MR4.0 (two consecutive measures separated by at least 4 weeks showing loss of MR4.0, corresponding to = BCR-ABL/ABL ≤ 0.01% IS).

For patients who fail to achieve MMR after three months of treatment reinitiation, BCR-ABL kinase domain mutation testing should be performed.

Monitoring of BCR-ABL Transcript Levels in Patients Who Have Reinitiated Therapy After Loss of Molecular Response

Monitor CBC and BCR-ABL transcripts in patients who reinitiate treatment with Tasigna due to loss of molecular response quantitation every 4 weeks until a major molecular response is re-established, then every 12 weeks.

6 ADVERSE REACTIONS

The following clinically significant adverse reactions can occur with Tasigna and are discussed in greater detail in other sections of labeling:

- Myelosuppression [see Warnings and Precautions (5.1)]
- QT Prolongation [see Boxed Warning, Warnings and Precautions (5.2)]
- Sudden Deaths [see Boxed Warning, Warnings and Precautions (5.3)]
- Cardiac and Arterial Vascular Occlusive Events [see Warnings and Precautions (5.4)]
- Pancreatitis and Elevated Serum Lipase [see Warnings and Precautions (5.5)]
- Hepatotoxicity [see Warnings and Precautions (5.6)]
- Electrolyte Abnormalities [see Boxed Warning, Warnings and Precautions (5.7)]
- Hemorrhage [see Warnings and Precautions (5.9)]
- Fluid Retention [see Warnings and Precautions (5.13)]

6.1 Clinical Trials Experience

Because clinical trials are conducted under widely varying conditions, adverse reaction rates observed in the clinical trials of a drug cannot be directly compared to rates in the clinical trials of another drug and may not reflect the rates observed in practice.

In Adult Patients With Newly Diagnosed Ph+ CML-CP

The data below reflect exposure to Tasigna from a randomized trial in patients with newly diagnosed Ph+ CML in chronic phase treated at the recommended dose of 300 mg twice daily (n = 279). The median time on treatment in the Tasigna 300 mg twice daily group was 61 months (range, 0.1 to 71 months). The median actual dose intensity was 593 mg/day in the Tasigna 300 mg twice daily group.

The most common (greater than 10%) non-hematologic adverse drug reactions were rash, pruritus, headache, nausea, fatigue, alopecia, myalgia, and upper abdominal pain. Constipation, diarrhea, dry skin, muscle spasms, arthralgia, abdominal pain, peripheral edema, vomiting, and asthenia were observed less commonly (less than or equal to 10% and greater than 5%) and have been of mild-to-moderate severity, manageable and generally did not require dose reduction.

Increase in QTcF greater than 60 msec from baseline was observed in 1 patient (0.4%) in the 300 mg twice daily treatment group. No patient had an absolute QTcF of greater than 500 msec while on study drug.

The most common hematologic adverse drug reactions (all Grades) were myelosuppression, including: thrombocytopenia (18%), neutropenia (15%), and anemia (8%). See Table 9 for Grade 3/4 laboratory abnormalities.

Discontinuation due to adverse reactions, regardless of relationship to study drug, was observed in 10% of patients.

In Adult Patients With Resistant or Intolerant Ph+ CML-CP and CML-AP

In the single-arm, open-label multicenter clinical trial, a total of 458 patients with Ph+ CML-CP and CML-AP resistant to or intolerant to at least one prior therapy, including imatinib were treated (CML-CP = 321; CML-AP = 137) at the recommended dose of 400 mg twice daily.

The median duration of exposure in days for CML-CP and CML-AP patients is 561 (range, 1 to 1096) and 264 (range, 2 to 1160), respectively. The median dose intensity for patients with CML-CP and CML-AP is 789 mg/day (range, 151 to 1110) and 780 mg/day (range, 150 to 1149), respectively, and corresponded to the planned 400 mg twice daily dosing.

The median cumulative duration in days of dose interruptions for the CML-CP patients was 20 (range, 1 to 345), and the median duration in days of dose interruptions for the CML-AP patients was 23 (range, 1 to 234).

In patients with CML-CP, the most commonly reported non-hematologic adverse drug reactions (greater than or equal to 10%) were rash, pruritus, nausea, fatigue, headache, constipation, diarrhea, vomiting, and myalgia. The common serious drug-related adverse reactions (greater than or equal to 1% and less than 10%) were thrombocytopenia, neutropenia, and anemia.

In patients with CML-AP, the most commonly reported non-hematologic adverse drug reactions (greater than or equal to 10%) were rash, pruritus and fatigue. The common serious adverse drug reactions (greater than or equal to 1% and less than 10%) were thrombocytopenia, neutropenia, febrile neutropenia, pneumonia, leukopenia, intracranial hemorrhage, elevated lipase, and pyrexia.

Sudden deaths and QT prolongation were reported. The maximum mean QTcF change from baseline at steady-state was 10 msec. Increase in QTcF greater than 60 msec from baseline was observed in 4.1% of the patients and QTcF of greater than 500 msec was observed in 4 patients (less than 1%) [see Boxed Warning, Warnings and Precautions (5.2, 5.3), Clinical Pharmacology (12.2)].

Discontinuation due to adverse drug reactions was observed in 16% of CML-CP and 10% of CML-AP patients.

Most Frequently Reported Adverse Reactions

Tables 7 and 8 show the percentage of adult patients experiencing non-hematologic adverse reactions (excluding laboratory abnormalities) regardless of relationship to study drug. Adverse reactions reported in greater than 10% of adult patients who received at least 1 dose of Tasigna are listed.

Table 7: Most Frequently Reported Non-Hematologic Adverse Reactions (Regardless of Relationship to Study Drug) in Adult Patients With Newly Diagnosed Ph+ CML-CP (greater than or equal to 10% in Tasigna 300 mg twice daily or imatinib 400 mg once daily groups) 60-Month Analysisa
 |  | Patients With Newly Diagnosed Ph+ CML-CP
 |  | Tasigna 300 mg twice daily | imatinib 400 mg once daily | Tasigna 300 mg twice daily | imatinib 400 mg once daily
 |  | N = 279 | N = 280 | N = 279 | N = 280
Body System and Adverse Reaction |  | All Grades (%) |  | CTC Gradesb 3/4 (%)
Skin and subcutaneous tissue disorders | Rash | 38 | 19 | < 1 | 2
 | Pruritus | 21 | 7 | < 1 | 0
 | Alopecia | 13 | 7 | 0 | 0
 | Dry skin | 12 | 6 | 0 | 0
Gastrointestinal disorders | Nausea | 22 | 41 | 2 | 2
 | Constipation | 20 | 8 | < 1 | 0
 | Diarrhea | 19 | 46 | 1 | 4
 | Vomiting | 15 | 27 | < 1 | < 1
 | Abdominal pain upper | 18 | 14 | 1 | < 1
 | Abdominal pain | 15 | 12 | 2 | 0
 | Dyspepsia | 10 | 12 | 0 | 0
Nervous system disorders | Headache | 32 | 23 | 3 | < 1
 | Dizziness | 12 | 11 | < 1 | < 1
General disorders and administration-site conditions | Fatigue | 23 | 20 | 1 | 1
 | Pyrexia | 14 | 13 | < 1 | 0
 | Asthenia | 14 | 12 | < 1 | 0
 | Peripheral edema | 9 | 20 | < 1 | 0
 | Face edema | < 1 | 14 | 0 | < 1
Musculoskeletal and connective tissue disorders | Myalgia | 19 | 19 | < 1 | < 1
 | Arthralgia | 22 | 17 | < 1 | < 1
 | Muscle spasms | 12 | 34 | 0 | 1
 | Pain in extremity | 15 | 16 | < 1 | < 1
 | Back pain | 19 | 17 | 1 | 1
Respiratory, thoracic, and mediastinal disorders | Cough | 17 | 13 | 0 | 0
 | Oropharyngeal pain | 12 | 6 | 0 | 0
 | Dyspnea | 11 | 6 | 2 | < 1
Infections and infestations | Nasopharyngitis | 27 | 21 | 0 | 0
 | Upper respiratory tract infection | 17 | 14 | < 1 | 0
 | Influenza | 13 | 9 | 0 | 0
 | Gastroenteritis | 7 | 10 | 0 | < 1
Eye disorders | Eyelid edema | 1 | 19 | 0 | < 1
 | Periorbital edema | < 1 | 15 | 0 | 0
Psychiatric disorders | Insomnia | 11 | 9 | 0 | 0
Vascular disorder | Hypertension | 10 | 4 | 1 | < 1
Abbreviations: CML-CP, chronic myeloid leukemia-chronic phase; Ph+, Philadelphia chromosome positive.
aExcluding laboratory abnormalities.
bNCI Common Terminology Criteria (CTC) for Adverse Events, version 3.0.

Table 8: Most Frequently Reported Non-Hematologic Adverse Reactions in Adult Patients With Resistant or Intolerant Ph+ CML Receiving Tasigna 400 mg Twice Daily (regardless of relationship to study drug) (greater than or equal to 10% in any group) 24-Month Analysisa
Body System and Adverse Reaction |  | CML-CP |  | CML-AP
 |  | N = 321 |  | N = 137
 |  | All Grades (%) | CTC Gradesb 3/4 (%) | All Grades (%) | CTC Gradesb 3/4 (%)
Skin and subcutaneous tissue disorders | Rash | 36 | 2 | 29 | 0
 | Pruritus | 32 | < 1 | 20 | 0
 | Night sweat | 12 | < 1 | 27 | 0
 | Alopecia | 11 | 0 | 12 | 0
Gastrointestinal disorders | Nausea | 37 | 1 | 22 | < 1
 | Constipation | 26 | < 1 | 19 | 0
 | Diarrhea | 28 | 3 | 24 | 2
 | Vomiting | 29 | < 1 | 13 | 0
 | Abdominal pain | 15 | 2 | 16 | 3
 | Abdominal pain upper | 14 | < 1 | 12 | < 1
 | Dyspepsia | 10 | < 1 | 4 | 0
Nervous system disorders | Headache | 35 | 2 | 20 | 1
General disorders and administration-site conditions | Fatigue | 32 | 3 | 23 | < 1
 | Pyrexia | 22 | < 1 | 28 | 2
 | Asthenia | 16 | 0 | 14 | 1
 | Peripheral edema | 15 | < 1 | 12 | 0
Musculoskeletal and connective tissue disorders | Myalgia | 19 | 2 | 16 | < 1
 | Arthralgia | 26 | 2 | 16 | 0
 | Muscle spasms | 13 | < 1 | 15 | 0
 | Bone pain | 14 | < 1 | 15 | 2
 | Pain in extremity | 20 | 2 | 18 | 1
 | Back pain | 17 | 2 | 15 | < 1
 | Musculoskeletal pain | 11 | < 1 | 12 | 1
Respiratory, thoracic, and mediastinal disorders | Cough | 27 | < 1 | 18 | 0
 | Dyspnea | 15 | 2 | 9 | 2
 | Oropharyngeal pain | 11 | 0 | 7 | 0
Infections and infestations | Nasopharyngitis | 24 | < 1 | 15 | 0
 | Upper respiratory tract infection | 12 | 0 | 10 | 0
Metabolism and nutrition disorders | Decreased appetitec | 15 | < 1 | 17 | < 1
Psychiatric disorders | Insomnia | 12 | 1 | 7 | 0
Vascular disorders | Hypertension | 10 | 2 | 11 | < 1
Abbreviations: CML-AP, chronic myeloid leukemia-accelerated phase; CML-CP, chronic myeloid leukemia-chronic phase; Ph+, Philadelphia chromosome positive.
aExcluding laboratory abnormalities.
bNCI Common Terminology Criteria for Adverse Events, version 3.0.
cAlso includes preferred term anorexia.

Laboratory Abnormalities

Table 9 shows the percentage of adult patients experiencing treatment-emergent Grade 3/4 laboratory abnormalities in patients who received at least one dose of Tasigna.

Table 9: Percent Incidence of Clinically Relevant Grade 3/4* Laboratory Abnormalities
 | Patient population
 | Newly diagnosed adult Ph+ CML-CP |  | Resistant or intolerant adult Ph+
 |  |  | CML-CP | CML-AP
 | Tasigna 300 mg twice daily N = 279 (%) | imatinib 400 mg once daily N = 280 (%) | Tasigna 400 mg twice daily N = 321 (%) | Tasigna 400 mg twice daily N = 137 (%)
Hematologic parameters
Thrombocytopenia | 10 | 9 | 30^1 | 42^3
Neutropenia | 12 | 22 | 31^2 | 42^4
Anemia | 4 | 6 | 11 | 27
Biochemistry parameters
Elevated lipase | 9 | 4 | 18 | 18
Hyperglycemia | 7 | < 1 | 12 | 6
Hypophosphatemia | 8 | 10 | 17 | 15
Elevated bilirubin (total) | 4 | < 1 | 7 | 9
Elevated SGPT (ALT) | 4 | 3 | 4 | 4
Hyperkalemia | 2 | 1 | 6 | 4
Hyponatremia | 1 | < 1 | 7 | 7
Hypokalemia | < 1 | 2 | 2 | 9
Elevated SGOT (AST) | 1 | 1 | 3 | 2
Decreased albumin | 0 | < 1 | 4 | 3
Hypocalcemia | < 1 | < 1 | 2 | 5
Elevated alkaline phosphatase | 0 | < 1 | < 1 | 1
Elevated creatinine | 0 | < 1 | < 1 | < 1
Abbreviations: ALT alanine aminotransferase; AST, aspartate aminotransferase; CML-AP, chronic myeloid leukemia-accelerated phase; CML-CP, chronic myeloid leukemia-chronic phase; Ph+, Philadelphia chromosome positive.
*NCI Common Terminology Criteria for Adverse Events, version 3.0.
^1CML-CP: Thrombocytopenia: 12% were Grade 3, 18% were Grade 4.
^2CML-CP: Neutropenia: 16% were Grade 3, 15% were Grade 4.
^3CML-AP: Thrombocytopenia: 11% were Grade 3, 32% were Grade 4.
^4CML-AP: Neutropenia: 16% were Grade 3, 26% were Grade 4.

Elevated total cholesterol (all Grades) occurred in 28% (Tasigna 300 mg twice daily) and 4% (imatinib). Elevated triglycerides (all Grades) occurred in 12% and 8% of patients in the Tasigna and imatinib arms, respectively. Hyperglycemia (all Grades) occurred in 50% and 31% of patients in the Tasigna and imatinib arms, respectively.

Most common biochemistry laboratory abnormalities (all Grades) were alanine aminotransferase increased (72%), blood bilirubin increased (59%), aspartate aminotransferase increased (47%), lipase increased (28%), blood glucose increased (50%), blood cholesterol increased (28%), and blood triglyceride increased (12%).

Treatment Discontinuation in Patients With Ph+ CML-CP Who Have Achieved a Sustained Molecular Response (MR4.5)

In eligible patients who discontinued Tasigna therapy after attaining a sustained molecular response (MR4.5), musculoskeletal symptoms (e.g., myalgia, pain in extremity, arthralgia, bone pain, spinal pain, or musculoskeletal pain), were reported more frequently than before treatment discontinuation in the first year, as noted in Table 10. The rate of new musculoskeletal symptoms generally decreased in the second year after treatment discontinuation.

In the newly diagnosed population in whom musculoskeletal symptoms occurred at any time during the TFR phase, 23/53 (43%) had not resolved by the TFR end date or data cut-off date. In the population previously treated with imatinib in whom musculoskeletal events occurred at any time during the TFR phase, 32/57 (56%) had not resolved by the data cut-off date.

The rate of musculoskeletal symptoms decreased in patients who entered the Tasigna treatment reinitiation (NTRI) phase, at 11/88 (13%) in the newly diagnosed population and 14/56 (25%) in the population previously treated with imatinib. Other adverse reactions observed in the Tasigna re-treatment phase were similar to those observed during Tasigna use in patients with newly diagnosed Ph+ CML-CP and resistant or intolerant Ph+ CML-CP and CML-AP.

Table 10: Musculoskeletal Symptoms Occurring Upon Treatment Discontinuation in the Context of Treatment-Free Remission (TFR)
 | Entire TFR period in all TFR patients |  |  |  | By time interval, in subset of patients in TFR greater than 48 weeks
Ph+ CML-CP patients | N | Median follow-up in TFR | Patients with musculoskeletal symptoms |  | N | Year prior to Tasigna discontinuation |  | 1st year after Tasigna discontinuation |  | 2nd year after Tasigna discontinuation
 |  |  | All Grades | Grade 3/4 |  | All Grades | Grade 3/4 | All Grades | Grade 3/4 | All Grades | Grade 3/4
Newly Diagnosed | 190 | 76 weeks | 28% | 1% | 100 | 17% | 0% | 34% | 2% | 9% | 0%
Previously treated with imatinib | 126 | 99 weeks | 45% | 2% | 73 | 14% | 0% | 48% | 3% | 15% | 1%
Abbreviations: CML-CP, chronic myeloid leukemia-chronic phase; Ph+, Philadelphia chromosome positive ; TFR, treatment-free remission.

Additional Data From Clinical Trials

The following adverse drug reactions were reported in adult patients in the Tasigna clinical studies at the recommended doses. These adverse drug reactions are ranked under a heading of frequency, the most frequent first using the following convention: common (greater than or equal to 1% and less than 10%), uncommon (greater than or equal to 0.1% and less than 1%), and unknown frequency (single events). For laboratory abnormalities, very common events (greater than or equal to 10%), which were not included in Tables 7 and 8, are also reported. These adverse reactions are included based on clinical relevance and ranked in order of decreasing seriousness within each category, obtained from 2 clinical studies:

1. Adult patients with newly diagnosed Ph+ CML-CP 60 month analysis and,

2. Adult patients with resistant or intolerant Ph+ CML-CP and CMP-AP 24 months’ analysis.

Infections and Infestations: Common: folliculitis. Uncommon: pneumonia, bronchitis, urinary tract infection, candidiasis (including oral candidiasis). Unknown frequency: hepatitis B reactivation, sepsis, subcutaneous abscess, anal abscess, furuncle, tinea pedis.

Neoplasms Benign, Malignant, and Unspecified: Common: skin papilloma. Unknown frequency: oral papilloma, paraproteinemia.

Blood and Lymphatic System Disorders: Common: leukopenia, eosinophilia, febrile neutropenia, pancytopenia, lymphopenia. Unknown frequency: thrombocythemia, leukocytosis.

Immune System Disorders: Unknown frequency: hypersensitivity.

Endocrine Disorders: Uncommon: hyperthyroidism, hypothyroidism. Unknown frequency: hyperparathyroidism secondary, thyroiditis.

Metabolism and Nutrition Disorders: Very Common: hypophosphatemia. Common: electrolyte imbalance (including hypomagnesemia, hyperkalemia, hypokalemia, hyponatremia, hypocalcemia, hypercalcemia, hyperphosphatemia), diabetes mellitus, hyperglycemia, hypercholesterolemia, hyperlipidemia, hypertriglyceridemia. Uncommon: gout, dehydration, increased appetite. Unknown frequency: hyperuricemia, hypoglycemia.

Psychiatric Disorders: Common: depression, anxiety. Unknown frequency: disorientation, confusional state, amnesia, dysphoria.

Nervous System Disorders: Common: peripheral neuropathy, hypoesthesia, paresthesia. Uncommon: intracranial hemorrhage, ischemic stroke, transient ischemic attack, cerebral infarction, migraine, loss of consciousness (including syncope), tremor, disturbance in attention, hyperesthesia, facial paralysis. Unknown frequency: basilar artery stenosis, brain edema, optic neuritis, lethargy, dysesthesia, restless legs syndrome.

Eye Disorders: Common: eye hemorrhage, eye pruritus, conjunctivitis, dry eye (including xerophthalmia). Uncommon: vision impairment, vision blurred, visual acuity reduced, photopsia, hyperemia (scleral, conjunctival, ocular), eye irritation, conjunctival hemorrhage. Unknown frequency: papilledema, diplopia, photophobia, eye swelling, blepharitis, eye pain, chorioretinopathy, conjunctivitis allergic, ocular surface disease.

Ear and Labyrinth Disorders: Common: vertigo. Unknown frequency: hearing impaired, ear pain, tinnitus.

Cardiac Disorders: Common: angina pectoris, arrhythmia (including atrioventricular block, cardiac flutter, extrasystoles, atrial fibrillation, tachycardia, bradycardia), palpitations, electrocardiogram QT prolonged. Uncommon: cardiac failure, myocardial infarction, coronary artery disease, cardiac murmur, coronary artery stenosis, myocardial ischemia, pericardial effusion, cyanosis. Unknown frequency: ventricular dysfunction, pericarditis, ejection fraction decrease.

Vascular Disorders: Common: flushing. Uncommon: hypertensive crisis, peripheral arterial occlusive disease, intermittent claudication, arterial stenosis limb, hematoma, arteriosclerosis. Unknown frequency: shock hemorrhagic, hypotension, thrombosis, peripheral artery stenosis.

Respiratory, Thoracic and Mediastinal Disorders: Common: dyspnea exertional, epistaxis, dysphonia. Uncommon: pulmonary edema, pleural effusion, interstitial lung disease, pleuritic pain, pleurisy, pharyngolaryngeal pain, throat irritation. Unknown frequency: pulmonary hypertension, wheezing.

Gastrointestinal Disorders: Common: pancreatitis, abdominal discomfort, abdominal distension, dysgeusia, flatulence. Uncommon: gastrointestinal hemorrhage, melena, mouth ulceration, gastroesophageal reflux, stomatitis, esophageal pain, dry mouth, gastritis, sensitivity of teeth. Unknown frequency: gastrointestinal ulcer perforation, retroperitoneal hemorrhage, hematemesis, gastric ulcer, esophagitis ulcerative, subileus, enterocolitis, hemorrhoids, hiatus hernia, rectal hemorrhage, gingivitis.

Hepatobiliary Disorders: Very common: hyperbilirubinemia. Common: hepatic function abnormal. Uncommon: hepatotoxicity, toxic hepatitis, jaundice. Unknown frequency: cholestasis, hepatomegaly.

Skin and Subcutaneous Tissue Disorders: Common: eczema, urticaria, erythema, hyperhidrosis, contusion, acne, dermatitis (including allergic, exfoliative and acneiform). Uncommon: exfoliative rash, drug eruption, pain of skin, ecchymosis. Unknown frequency: psoriasis, erythema multiforme, erythema nodosum, skin ulcer, palmar-plantar erythrodysesthesia syndrome, petechiae, photosensitivity, blister, dermal cyst, sebaceous hyperplasia, skin atrophy, skin discoloration, skin exfoliation, skin hyperpigmentation, skin hypertrophy, hyperkeratosis.

Musculoskeletal and Connective Tissue Disorders: Common: bone pain, musculoskeletal chest pain, musculoskeletal pain, back pain, neck pain, flank pain, muscular weakness. Uncommon: musculoskeletal stiffness, joint swelling. Unknown frequency: arthritis.

Renal and Urinary Disorders: Common: pollakiuria. Uncommon: dysuria, micturition urgency, nocturia. Unknown frequency: renal failure, hematuria, urinary incontinence, chromaturia.

Reproductive System and Breast Disorders: Uncommon: breast pain, gynecomastia, erectile dysfunction. Unknown frequency: breast induration, menorrhagia, nipple swelling.

General Disorders and Administration Site Conditions: Common: pyrexia, chest pain (including non-cardiac chest pain), pain, chest discomfort, malaise. Uncommon: gravitational edema, influenza-like illness, chills, feeling body temperature change (including feeling hot, feeling cold). Unknown frequency: localized edema.

Investigations: Very Common: alanine aminotransferase increased, aspartate aminotransferase increased, lipase increased, lipoprotein cholesterol (including very low density and high density) increased, total cholesterol increased, blood triglycerides increased. Common: hemoglobin decreased, blood amylase increased, gamma-glutamyltransferase increased, blood creatinine phosphokinase increased, blood alkaline phosphatase increased, weight decreased, weight increased, globulins decreased. Uncommon: blood lactate dehydrogenase increased, blood urea increased. Unknown frequency: troponin increased, blood bilirubin unconjugated increased, insulin C-peptide decreased, blood parathyroid hormone increased.

In Pediatric Patients With Newly Diagnosed Ph+ CML-CP or Resistant or Intolerant Ph+ CML-CP

The data below reflect exposure to Tasigna from two studies in pediatric patients from 2 to less than 18 years of age with either newly diagnosed Ph+ CML-CP or imatinib/dasatinib resistant or intolerant Ph+ CML-CP treated at the recommended dose of 230 mg/m^2 twice daily (n = 69) [see Clinical Studies (14.5)]. The median time on treatment with Tasigna was 39.6 months (range, 0.7 to 63.5 months). The median actual dose intensity was 427.7 mg/m^2/day (range 149.1 to 492.8 mg/m^2/day), and the median relative dose intensity was 93% (range, 32.4 to 107.1%). Thirty-nine patients (57%) had relative dose intensity superior to 90%.

In pediatric patients with Ph+ CML-CP, the most common (greater than 20%) non-hematologic adverse reactions were hyperbilirubinemia, headache, alanine aminotransferase increased, rash, pyrexia, nausea, aspartate aminotransferase increased, pain in extremity, upper respiratory tract infection, vomiting, diarrhea, and nasopharyngitis. The most common (greater than 5%) Grade 3/4 non-hematologic adverse reactions were hyperbilirubinemia, rash, alanine aminotransferase increased, and neutropenia.

Laboratory abnormalities of hyperbilirubinemia (Grade 3/4: 16%) and transaminase elevation (AST Grade 3/4: 2.9%, ALT Grade 3/4: 10%), were reported at a higher frequency than in adult patients.

The most common hematological laboratory abnormalities (greater than or equal to 30% of patients, of all Grades) were decreases in total white blood cells (54%), platelet count (44%), absolute neutrophils (44%), hemoglobin (38%), and absolute lymphocytes (36%).

Discontinuation of study treatment due to adverse reactions occurred in 15 patients (22%). The most frequent adverse reactions leading to discontinuation were hyperbilirubinemia (9%) and rash (6%).

Increase in QTcF greater than 30 msec from baseline was observed in 19 patients (28%). No patient had an absolute QTcF of greater than 500 msec or QTcF increase of greater than 60 msec from baseline.

Growth Retardation in Pediatric Population

In a multicenter, open-label, single-arm study of 58 pediatric patients with newly diagnosed or resistant Ph+ CML-CP treated with Tasigna, with a median exposure of 56.7 months, adverse reactions associated with growth and deceleration of growth in regard to height were reported in 3 patients (5%). The adverse reactions include growth retardation in 2 adolescent patients and growth hormone deficiency with short stature in the remaining patient (age category: child). Of the 58 pediatric patients, five (9%) crossed two main percentile lines from baseline and three (5%) crossed three main percentile lines from baseline (percentile lines: 5th, 10th, 25th, 50th, 75th, 90th, and 95th). Close monitoring of growth in pediatric patients under Tasigna treatment is recommended [see Warnings and Precautions (5.14)].

6.2 Postmarketing Experience

The following adverse reactions have been identified during postapproval use of Tasigna. Because these reactions are reported voluntarily from a population of uncertain size, it is not always possible to reliably estimate their frequency or establish a causal relationship to drug exposure.

Blood and Lymphatic System Disorders: thrombotic microangiopathy

Nervous System Disorders: facial paralysis

Musculoskeletal and Connective Tissue Disorders: osteonecrosis

7 DRUG INTERACTIONS

7.1 Effect of Other Drugs on Tasigna

Strong CYP3A Inhibitors

Concomitant use with a strong CYP3A inhibitor increased nilotinib concentrations compared to Tasigna alone [see Clinical Pharmacology (12.3)], which may increase the risk of Tasigna toxicities. Avoid concomitant use of strong CYP3A inhibitors with Tasigna. If patients must be coadministered a strong CYP3A4 inhibitor, reduce Tasigna dose [see Dosage and Administration (2.8)].

Strong CYP3A Inducers

Concomitant use with a strong CYP3A inducer decreased nilotinib concentrations compared to Tasigna alone [see Clinical Pharmacology (12.3)], which may reduce Tasigna efficacy. Avoid concomitant use of strong CYP3A inducers with Tasigna.

Proton Pump Inhibitors

Concomitant use with a proton pump inhibitor (PPI) decreased nilotinib concentrations compared to Tasigna alone [see Clinical Pharmacology (12.3)], which may reduce Tasigna efficacy. Avoid concomitant use of PPI with Tasigna. As an alternative to PPIs, use H2 blockers approximately 10 hours before or approximately 2 hours after the dose of Tasigna, or use antacids approximately 2 hours before or approximately 2 hours after the dose of Tasigna.

7.2 Drugs That Prolong the QT Interval

Avoid coadministration of Tasigna with agents that may prolong the QT interval, such as anti-arrhythmic drugs [see Boxed Warning, Dosage and Administration (2.4), Warnings and Precautions (5.2), Drug Interactions (7.1), Clinical Pharmacology (12.2)].

8 USE IN SPECIFIC POPULATIONS

8.1 Pregnancy

Risk Summary

Based on findings from animal studies and the mechanism of action, Tasigna can cause fetal harm when administered to a pregnant woman [see Clinical Pharmacology (12.1)]. There are no available data in pregnant women to inform the drug-associated risk. In animal reproduction studies, administration of nilotinib to pregnant rats and rabbits during organogenesis caused adverse developmental outcomes, including embryo-fetal lethality, fetal effects, and fetal variations in rats and rabbits at maternal exposures (AUC) approximately 2 and 0.5 times, respectively, the exposures in patients at the recommended dose (see Data). Advise pregnant women of the potential risk to a fetus.

The background risk of major birth defects and miscarriage for the indicated population is unknown. All pregnancies have a background risk of birth defect, loss, or other adverse outcomes. In the U.S. general population, the estimated background risk of major birth defects and miscarriage in clinically recognized pregnancies are 2% to 4% and 15% to 20%, respectively.

Data

Animal Data

In embryo-fetal development studies in rats and rabbits, pregnant animals received oral doses of nilotinib up to 100 mg/kg/day and 300 mg/kg/day, respectively, during the period of organogenesis.

In rats, oral administration of nilotinib produced embryo-lethality/fetal effects at doses ≥ 30 mg/kg/day. At ≥ 30 mg/kg/day, skeletal variations of incomplete ossification of the frontals and misshapen sternebra were noted, and there was an increased incidence of small renal papilla and fetal edema. At 100 mg/kg/day, nilotinib was associated with maternal toxicity (decreased gestation weight, gravid uterine weight, net weight gain, and food consumption) and resulted in a single incidence of cleft palate and two incidences of pale skin were noted in the fetuses. A single incidence of dilated ureters was noted in a fetus also displaying small renal papilla at 100 mg/kg/day. Additional variations of forepaw and hindpaw phalanx unossified, fused sternebra, bipartite sternebra ossification, and incomplete ossification of the cervical vertebra were noted at 100 mg/kg/day.

In rabbits, oral administration of nilotinib resulted in the early sacrifice of two females, maternal toxicity and increased resorption of fetuses at 300 mg/kg/day. Fetal skeletal variations (incomplete ossification of the hyoid, bent hyoid, supernumerary short detached ribs and the presence of additional ossification sites near the nasals, frontals and in the sternebral column) were also increased at this dose in the presence of maternal toxicity. Slight maternal toxicity was evident at 100 mg/kg/day but there were no reproductive or embryo-fetal effects at this dose.

At 30 mg/kg/day in rats and 300 mg/kg/day in rabbits, the maternal systemic exposure (AUC) were 72700 ng*hr/mL and 17100 ng*hr/mL, respectively, representing approximately 2 and 0.5 times the exposure in humans at the highest recommended dose 400 mg twice daily.

When pregnant rats were dosed with nilotinib during organogenesis and through lactation, the adverse effects included a longer gestational period, lower pup body weights until weaning and decreased fertility indices in the pups when they reached maturity, all at a maternal dose of 60 mg/kg (i.e., 360 mg/m^2, approximately 0.7 times the clinical dose of 400 mg twice daily based on body surface area). At doses up to 20 mg/kg (i.e., 120 mg/m^2, approximately 0.25 times the clinical dose of 400 mg twice daily based on body surface area) no adverse effects were seen in the maternal animals or the pups.

8.2 Lactation

Risk Summary

There are no data on the presence of nilotinib or its metabolites in human milk or its effects on a breastfed child or on milk production. However, nilotinib is present in the milk of lactating rats. Because of the potential for serious adverse reactions in a breastfed child, advise women not to breastfeed during treatment with Tasigna and for 14 days after the last dose.

Animal Data

After a single 20 mg/kg of [^14C] nilotinib dose to lactating rats, the transfer of parent drug and its metabolites into milk was observed. The overall milk-to-plasma exposure ratio of total radioactivity was approximately 2, based on the AUC0-24h or AUC0-INF values. No rat metabolites of nilotinib were detected that were unique to milk.

8.3 Females and Males of Reproductive Potential

Based on animal studies, Tasigna can cause fetal harm when administered to a pregnant woman [see Use in Specific Populations (8.1)].

Pregnancy Testing

Females of reproductive potential should have a pregnancy test prior to starting treatment with Tasigna.

Contraception

Females

Advise females of reproductive potential to use effective contraception during treatment with Tasigna and for 14 days after the last dose.

Infertility

The risk of infertility in females or males of reproductive potential has not been studied in humans. In studies in rats and rabbits, the fertility in males and females was not affected [see Nonclinical Toxicology (13.1)].

8.4 Pediatric Use

The safety and effectiveness of Tasigna have been established in pediatric patients greater than or equal to 1 year of age with newly diagnosed and resistant or intolerant Ph+ CML in chronic phase [see Clinical Studies (14.5)]. There are no data for pediatric patients under 2 years of age. Use of Tasigna in pediatric patients 1 year to less than 2 years of age with newly diagnosed or resistant or intolerant Ph+ CML in chronic phase is supported by efficacy in pediatric patients 2 to 6 years of age for these indications. The safety and effectiveness of Tasigna have been established in pediatric patients greater than or equal to 1 year of age with resistant or intolerant Ph+ CML in accelerated phase based on evidence of effectiveness from an adequate and well-controlled single-arm study in adults [see Clinical Studies (14.2)] with safety data from two pediatric studies as described in the next paragraph.

Use of Tasigna in pediatric patients 1 to less than 18 years of age is supported by evidence from two clinical trials [see Clinical Studies (14.5)]. The 25 patients with newly diagnosed Ph+ CML-CP were in the following age groups: 6 children (age 2 to less than 12 years) and 19 adolescents (age 12 to less than 18 years). The 44 patients with resistant or intolerant Ph+ CML-CP included 18 children (age 2 to less than 12 years) and 26 adolescents (age 12 to less than 18 years). All pediatric patients received Tasigna treatment at a dose of 230 mg/m^2 twice daily, rounded to the nearest 50 mg dose (to a maximum single dose of 400 mg). No differences in efficacy or safety were observed between the different age subgroups in the two trials.

The frequency, type, and severity of adverse reactions observed were generally consistent with those observed in adults, with the exception of the laboratory abnormalities of hyperbilirubinemia (Grade 3/4: 16%) and transaminase elevation (AST Grade 3/4: 2.9%, ALT Grade 3/4: 10%), which were reported at a higher frequency in pediatric patients than in adults [see Adverse Reactions (6.1)]. For pediatric growth and development, growth retardation has been reported in pediatric patients with Ph+ CML-CP treated with Tasigna [see Warnings and Precautions (5.14), Adverse Reactions (6.1)].

The safety and effectiveness of Tasigna in pediatric patients below the age of 1 year with newly diagnosed, or resistant or intolerant Ph+ CML in chronic phase and accelerated phase, have not been established.

8.5 Geriatric Use

In the clinical trials of Tasigna (patients with newly diagnosed Ph+ CML-CP and resistant or intolerant Ph+ CML-CP and CML-AP), approximately 12% and 30% of patients were 65 years or over, respectively.

- Patients with newly diagnosed Ph+ CML-CP: There was no difference in major molecular response between patients aged less than 65 years and those greater than or equal to 65 years.
- Patients with resistant or intolerant CML-CP: There was no difference in major cytogenetic response rate between patients aged less than 65 years and those greater than or equal to 65 years.
- Patients with resistant or intolerant CML-AP: The hematologic response rate was 44% in patients less than 65 years of age and 29% in patients greater than or equal to 65 years.

No major differences for safety were observed in patients greater than or equal to 65 years of age as compared to patients less than 65 years.

8.6 Cardiac Disorders

In the clinical trials, patients with a history of uncontrolled or significant cardiovascular disease, including recent myocardial infarction, congestive heart failure, unstable angina or clinically significant bradycardia, were excluded. Caution should be exercised in patients with relevant cardiac disorders [see Boxed Warning, Warnings and Precautions (5.2)].

8.7 Hepatic Impairment

Reduce the Tasigna dosage in patients with hepatic impairment and monitor the QT interval closely in these patients [see Dosage and Administration (2.7), Clinical Pharmacology (12.3)].

10 OVERDOSAGE

Overdose with nilotinib has been reported, where an unspecified number of Tasigna capsules were ingested in combination with alcohol and other drugs. Events included neutropenia, vomiting, and drowsiness. In the event of overdose, observe the patient and provide appropriate supportive treatment.

11 DESCRIPTION

Tasigna contains nilotinib, which belongs to a pharmacologic class of drugs known as kinase inhibitors.

Nilotinib drug substance, in the form of monohydrochloride monohydrate, is a white to slightly yellowish to slightly greenish yellow powder with the molecular formula and weight, respectively, of C28H22F3N7O•HCl • H2O and 584 g/mol (corresponding molecular formula and weight of nilotinib base, anhydrous are C28H22F3N7O and 529 g/mol, respectively). The solubility of nilotinib in aqueous solutions decreases with increasing pH. Nilotinib is not optically active. The pKa1 was determined to be 2.1; pKa2 was estimated to be 5.4.

The chemical name of nilotinib monohydrochloride monohydrate is 4-methyl-N-[3-(4-methyl-1H-imidazol-1-yl)-5-(trifluoromethyl)phenyl]-3-[[4-(3-pyridinyl)-2-pyrimidinyl]amino]-benzamide, monohydrochloride, monohydrate. Its structure is shown below:

Tasigna (nilotinib) capsules, for oral use, contain 50 mg, 150 mg, or 200 mg nilotinib base, anhydrous (equivalent to 55 mg, 166 mg, and 221 mg nilotinib monohydrochloride monohydrate respectively) with the following inactive ingredients: colloidal silicon dioxide, crospovidone, lactose monohydrate, magnesium stearate, and poloxamer 188. The capsules contain gelatin, iron oxide (red), iron oxide (yellow), iron oxide (black), and titanium dioxide.

12 CLINICAL PHARMACOLOGY

12.1 Mechanism of Action

Nilotinib is an inhibitor of the BCR-ABL kinase. Nilotinib binds to and stabilizes the inactive conformation of the kinase domain of ABL protein. In vitro, nilotinib inhibited BCR-ABL mediated proliferation of murine leukemic cell lines and human cell lines derived from patients with Ph+ CML. Under the conditions of the assays, nilotinib was able to overcome imatinib resistance resulting from BCR-ABL kinase mutations, in 32 out of 33 mutations tested. Nilotinib inhibited the autophosphorylation of the following kinases at IC50 values as indicated: BCR-ABL (20 to 60 nM), PDGFR (69 nM), c-KIT (210 nM), CSF-1R (125 to 250 nM), and DDR1 (3.7 nM).

12.2 Pharmacodynamics

Based on exposure-response analyses for efficacy, a relationship between drug exposure and a greater likelihood of response was observed in clinical studies. Based on exposure-response analyses for safety, a relationship between exposure and a greater likelihood of safety events, including a higher occurrence of total bilirubin elevations, was observed in clinical studies.

Cardiac Electrophysiology

Tasigna is associated with concentration-dependent QT prolongation. At a dose of Tasigna 400 mg twice daily given without food in healthy subjects, the maximum mean placebo-adjusted QTcF changes were 10.4 msec (90% CI: 2.85, 18.0). After a single dose of Tasigna 800 mg (two times the maximum approved recommended dosage) given with a high fat meal to healthy subjects, the maximum mean placebo-adjusted QTcF changes were) 18.0 msec (90% CI: 9.65, 25.8). Peak plasma concentrations in the QT study were 26% lower than or comparable with those observed in patients enrolled in the single-arm study [see Boxed Warning, Warnings and Precautions (5.2), Adverse Reactions (6.1)].

12.3 Pharmacokinetics

Steady-state nilotinib exposure was dose-dependent with less than dose-proportional increases in systemic exposure at dose levels higher than 400 mg given as once or twice daily dosing. In adult patients with resistant or intolerant Ph+ CML given Tasigna 400 mg twice daily, the steady-state mean (% CV) Cmax and AUC0-12h were 2260 ng/mL (35%) and 18000 ng∙h/mL (33%), respectively. In adult patients with newly diagnosed Ph+ CML given Tasigna 300 mg twice daily, the steady-state mean (% CV) Cmax and AUC0-12h were 1540 ng/mL (48%) and 13337 ng∙h/mL (46%), respectively.

Steady state conditions were achieved by Day 8. An increase in serum exposure to nilotinib between the first dose and steady state was approximately 2-fold for daily dosing and 3.8-fold for twice daily dosing. The average steady state nilotinib trough and peak concentrations did not change over 12 months.

Absorption

Relative bioavailability of nilotinib capsule is approximately 50%, as compared to an oral drink solution (pH of 1.2 to 1.3). Peak concentrations of nilotinib are reached 3 hours after oral administration. Nilotinib is a substrate of P-gp in vitro.

Median steady-state trough concentration of nilotinib was decreased by 53% in patients with total gastrectomy compared to patients who had not undergone surgeries [see Warnings and Precautions (5.10)].

Effect of Food

Compared to the fasted state, the systemic exposure (AUC) increased by 82% when the dose was given 30 minutes after a high fat meal (meal of 800 to 1000 calories with fat being 50% of total caloric content; approximately: 150 calories from protein, 250 calories from carbohydrates, and 500-600 calories from fat).

Single dose administration of two 200 mg nilotinib capsules each dispersed in 1 teaspoon of applesauce and administered within 15 minutes was shown to be bioequivalent to a single dose administration of two 200 mg intact capsules.

Distribution

The blood-to-serum ratio of nilotinib is 0.68. Serum protein binding is approximately 98%.

Elimination

The mean (CV%) apparent elimination half-life is estimated to be approximately 17 hours (69%) and the mean (CV%) apparent clearance approximates 29 L/h (61%).

Metabolism

Nilotinib is primarily metabolized via CYP3A4-mediated oxidation and to a minor extent by CYP2C8. Nilotinib is the main circulating component in the serum. None of the metabolites contribute significantly to the pharmacological activity of nilotinib.

Excretion

After a single dose of radiolabeled nilotinib, more than 90% of the administered dose was eliminated within 7 days: 93% of the dose in feces. Parent drug accounted for 69% of the dose.

Specific Populations

Age, sex, race/ethnicity, or body weight did not significantly affect the pharmacokinetics of nilotinib. The effect of renal impairment on nilotinib pharmacokinetics is unknown.

Pediatric Patients

Following administration of the approved recommend pediatric dosage of nilotinib, steady-state exposure of nilotinib were within 2-fold to adult patients treated with 400 mg twice daily. Steady-state Cmin was comparable across all age groups (pediatric patients from ages 2 to less than 18 years), diseases (patients with newly diagnosed and resistant or intolerant Ph+ CML) and studies.

Body surface area correlated with nilotinib clearance and was the primary factor responsible for the PK differences between pediatrics and adults.

Patients with Hepatic Impairment

Following a single dose of Tasigna 200 mg (0.5 times the maximum approved recommended dosage), the mean AUC of nilotinib increased 1.4-fold, 1.4-fold, and 1.6-fold in subjects with mild (Child-Pugh class A), moderate (Child-Pugh class B) and severe (Child-Pugh class C) hepatic impairment, respectively, compared to subjects with normal hepatic function.

Drug Interaction Studies

Clinical Studies

Strong CYP3A Inhibitors: Coadministration of ketoconazole (a strong CYP3A inhibitor) 400 mg once daily for 6 days increased nilotinib AUC by approximately 3-fold. A single concurrent intake of double-strength grapefruit juice increased the nilotinib AUC by 1.3-fold.

Strong CYP3A Inducers: Coadministration of rifampicin (a strong CYP3A inducer) 600 mg daily for 12 days decreased nilotinib AUC by approximately 80%.

Proton Pump Inhibitors (PPIs): Tasigna displays pH-dependent aqueous solubility. Coadministration of multiple doses of esomeprazole (a PPI) at 40 mg daily decreased the nilotinib AUC by 34%. No significant change in nilotinib pharmacokinetics was observed when a single 400 mg dose of Tasigna was administered 10 hours after and 2 hours before famotidine (an H2 blocker), or administered 2 hours after and 2 hours before an antacid (e.g., aluminum hydroxide, magnesium hydroxide, simethicone).

Moderate CYP3A Inhibitors: Following coadministration of nilotinib 400 mg twice daily with imatinib (a moderate CYP3A inhibitor) 400 mg daily or 400 mg twice daily, the AUC increased 30% to 50% for nilotinib and approximately 20% for imatinib.

CYP3A4 Substrates: Multiple doses of Tasigna increased the systemic exposure of oral midazolam (a substrate of CYP3A4) 2.6-fold.

CYP2C9 Substrates: Single-dose of Tasigna did not change the pharmacokinetics and pharmacodynamics of warfarin (a CYP2C9 substrate).

In Vitro Studies Where Drug Interaction Potential was not Further Evaluated Clinically

CYP Substrates: Nilotinib is a competitive inhibitor of CYP2C8, CYP2D6, and is an inducer of CYP2B6 and CYP2C8.

Substrates of Transporters: Nilotinib is an inhibitor of UGT1A1 and P-gp.

12.5 Pharmacogenomics

Tasigna can increase bilirubin levels. The (TA)7/(TA)7 genotype of UGT1A1 was associated with a statistically significant increase in the risk of hyperbilirubinemia relative to the (TA)6/(TA)6 and (TA)6/(TA)7 genotypes. However, the largest increases in bilirubin were observed in the (TA)7/(TA)7 genotype (UGT1A1*28) patients [see Warnings and Precautions (5.6)].

13 NONCLINICAL TOXICOLOGY

13.1 Carcinogenesis, Mutagenesis, Impairment of Fertility

A 2-year carcinogenicity study was conducted orally in rats at nilotinib doses of 5, 15, and 40 mg/kg/day. Exposures in animals at the highest dose tested were approximately 2- to 3-fold the human exposure (based on AUC) at the nilotinib dose of 400 mg twice daily. The study was negative for carcinogenic findings. A 26-week carcinogenicity study was conducted orally in Tg.rasH2 mice, a model genetically modified to enhance susceptibility to neoplastic transformation, at nilotinib doses of 30, 100, and 300 mg/kg/day. Nilotinib induced in the skin and subcutis statistically significant increases in the incidence of papillomas in females and of papillomas and combined papillomas and carcinomas in males at 300 mg/kg/day. The no-observed-adverse-effect-level (NOAEL) for skin neoplastic lesions was 100 mg/kg/day.

Nilotinib was not mutagenic in a bacterial mutagenesis (Ames) assay, was not clastogenic in a chromosome aberration assay in human lymphocytes, did not induce DNA damage (comet assay) in L5178Y mouse lymphoma cells, nor was it clastogenic in an in vivo rat bone marrow micronucleus assay with two oral treatments at doses up to 2000 mg/kg/dose.

There were no effects on male or female rat and female rabbit mating or fertility at doses up to 180 mg/kg in rats (approximately 4- to 7-fold for males and females, respectively, the AUC in patients at the dose of 400 mg twice daily) or 300 mg/kg in rabbits (approximately one-half the AUC in patients at the dose of 400 mg twice daily). The effect of Tasigna on human fertility is unknown. In a study where male and female rats were treated with nilotinib at oral doses of 20 to 180 mg/kg/day (approximately 1- to 6.6-fold the AUC in patients at the dose of 400 mg twice daily) during the pre-mating and mating periods and then mated, and dosing of pregnant rats continued through gestation Day 6, nilotinib increased post-implantation loss and early resorption, and decreased the number of viable fetuses and litter size at all doses tested.

14 CLINICAL STUDIES

14.1 Adult Newly Diagnosed Ph+ CML-CP

The ENESTnd (Evaluating Nilotinib Efficacy and Safety in clinical Trials-Newly Diagnosed patients) study (NCT00471497) was an open-label, multicenter, randomized trial conducted to determine the efficacy of Tasigna versus imatinib tablets in adult patients with cytogenetically confirmed newly diagnosed Ph+ CML-CP. Patients were within 6 months of diagnosis and were previously untreated for CML-CP, except for hydroxyurea and/or anagrelide. Efficacy was based on a total of 846 patients: 283 patients in the imatinib 400 mg once daily group, 282 patients in the Tasigna 300 mg twice daily group, 281 patients in the Tasigna 400 mg twice daily group.

Median age was 46 years in the imatinib group and 47 years in both Tasigna groups, with 12%, 13%, and 10% of patients greater than or equal to 65 years of age in imatinib 400 mg once daily, Tasigna 300 mg twice daily and Tasigna 400 mg twice daily treatment groups, respectively. There were slightly more male than female patients in all groups (56%, 56%, and 62% in imatinib 400 mg once daily, Tasigna 300 mg twice daily and Tasigna 400 mg twice daily treatment groups, respectively). More than 60% of all patients were Caucasian, and 25% were Asian.

The primary data analysis was performed when all 846 patients completed 12 months of treatment (or discontinued earlier). Subsequent analyses were done when patients completed 24, 36, 48, and 60 months of treatment (or discontinued earlier). The median time on treatment was approximately 61 months in all three treatment groups.

The primary efficacy endpoint was major molecular response (MMR) at 12 months after the start of study medication. MMR was defined as less than or equal to 0.1% BCR-ABL/ABL % by international scale measured by RQ-PCR, which corresponds to a greater than or equal to 3 log reduction of BCR-ABL transcript from standardized baseline. Efficacy endpoints are summarized in Table 11.

Two patients in the Tasigna arm progressed to either accelerated phase or blast crisis (both within the first 6 months of treatment) while 12 patients on the imatinib arm progressed to either accelerated phase or blast crisis (7 patients within first 6 months, 2 patients within 6 to 12 months, 2 patients within 12 to 18 months and 1 patient within 18 to 24 months).

Table 11: Efficacy (MMR and CCyR) of Tasigna Compared to imatinib in Adult Newly Diagnosed Ph+ CML-CP (ENESTnd)
 | Tasigna 300 mg twice daily | imatinib 400 mg once daily
 | N = 282 | N = 283
MMR at 12 months (95% CI) | 44% (38.4, 50.3) | 22% (17.6, 27.6)
P-Valuea | < 0.0001
CCyRb by 12 months (95% CI) | 80% (75.0, 84.6) | 65% (59.2, 70.6)
MMR at 24 months (95% CI) | 62% (55.8, 67.4) | 38% (31.8, 43.4)
CCyRb by 24 months (95% CI) | 87% (82.4, 90.6) | 77% (71.7, 81.8)
Abbreviation: CI, confidence interval.
aCMH test stratified by Sokal risk group.
bCCyR: 0% Ph+ metaphases. Cytogenetic responses were based on the percentage of Ph+ metaphases among greater than or equal to 20 metaphase cells in each bone marrow sample.

By the 60 months, MMR was achieved by 77% of patients on Tasigna and 60% of patients on imatinib; MR4.5 was achieved by 53.5% of patients on Tasigna and 31.4% on imatinib. Median overall survival was not reached in either arm. At the time of the 60-month final analysis, the estimated survival rate was 93.7% for patients on Tasigna and 91.7% for patients on imatinib.

14.2 Adult Patients With Resistant or Intolerant Ph+ CML-CP and CML-AP

Study CAMN107A2101 (referred to as Study A2101) (NCT00109707) was a single-arm, open-label, multicenter study conducted to evaluate the efficacy and safety of Tasigna (400 mg twice daily) in patients with imatinib-resistant or -intolerant CML with separate cohorts for chronic and accelerated phase disease. The definition of imatinib resistance included failure to achieve a complete hematologic response (by 3 months), cytogenetic response (by 6 months) or major cytogenetic response (by 12 months) or progression of disease after a previous cytogenetic or hematologic response. Imatinib intolerance was defined as discontinuation of treatment due to toxicity and lack of a major cytogenetic response at time of study entry. At the time of data cut-off, 321 patients with CML-CP and 137 patients with CML-AP with a minimum follow-up of 24 months were enrolled. In this study, about 50% of CML-CP and CML-AP patients were males, over 90% (CML-CP) and 80% (CML-AP) were Caucasian, and approximately 30% were age 65 years or older.

Overall, 73% of patients were imatinib resistant while 27% were imatinib intolerant. The median time of prior imatinib treatment was approximately 32 (CML-CP) and 28 (CML-AP) months. Prior therapy included hydroxyurea in 85% of patients, interferon in 56% and stem cell or bone marrow transplant in 8%. The median highest prior imatinib dose was 600 mg per day for patients with CML-CP and CML-AP, and the highest prior imatinib dose was greater than or equal to 600 mg/day in 74% of all patients with 40% of patients receiving imatinib doses greater than or equal to 800 mg/day.

Median duration of Tasigna treatment was 18.4 months in patients with CML-CP and 8.7 months in patients with CML-AP.

The efficacy endpoint in CML-CP was unconfirmed major cytogenetic response (MCyR) which included complete and partial cytogenetic responses.

The efficacy endpoint in CML-AP was confirmed hematologic response (HR), defined as either a complete hematologic response (CHR) or no evidence of leukemia (NEL). The rates of response for CML-CP and CML-AP patients are reported in Table 12.

Median durations of response had not been reached at the time of data analysis.

Table 12: Efficacy of Tasigna in Adult Resistant or Intolerant Ph+ CML-CP and CML-AP (Study A2101)
Cytogenetic response rate (unconfirmed) (%)a
 | Chronic phase (n = 321)
Major (95% CI) | 51% (46% – 57%)
Complete (95% CI) | 37% (32% – 42%)
Partial (95% CI) | 15% (11% – 19%)
 | Accelerated phase (n = 137)
Hematologic response rate (confirmed) (95% CI) b | 39% (31% – 48%)
Complete hematologic response rate (95% CI) | 30% (22% – 38%)
No evidence of leukemia (95% CI) | 9% (5% – 16%)
aCytogenetic response criteria: Complete (0% Ph+ metaphases) or partial (1% to 35%). Cytogenetic responses were based on the percentage of Ph-positive metaphases among greater than or equal to 20 metaphase cells in each bone marrow sample.
bHematologic response = CHR + NEL (all responses confirmed after 4 weeks).

CHR (CML-CP): WBC less than 10 x 10^9/L, platelets less than 450,000/mm^3, no blasts or promyelocytes in peripheral blood, less than 5% myelocytes + metamyelocytes in bone marrow, less than 20% basophils in peripheral blood, and no extramedullary involvement.

CHR (CML-AP): neutrophils greater than or equal to 1.5 x 10^9/L, platelets greater than or equal to 100 x 10^9/L, no myeloblasts in peripheral blood, myeloblasts less than 5% in bone marrow, and no extramedullary involvement.

NEL: same criteria as for CHR but neutrophils greater than or equal to 1.0 x 10^9/L and platelets greater than or equal to 20 x 10^9/L without transfusions or bleeding.

Adult Patients With Chronic Phase

The MCyR rate in 321 CML-CP patients was 51%. The median time to MCyR among responders was 2.8 months (range, 1 to 28 months). The median duration of MCyR cannot be estimated. The median duration of exposure on this single arm-trial was 18.4 months. Among the CML-CP patients who achieved MCyR, 62% of them had MCyR lasting more than 18 months. The CCyR rate was 37%.

Adult Patients With Accelerated Phase

The overall confirmed hematologic response rate in 137 patients with CML-AP was 39%. The median time to first hematologic response among responders was 1 month (range, 1 to 14 months). Among the CML-AP patients who achieved HR, 44% of them had a response lasting for more than 18 months.

After imatinib failure, 24 different BCR-ABL mutations were noted in 42% of chronic phase and 54% of accelerated phase CML patients who were evaluated for mutations.

14.3 Treatment Discontinuation in Newly Diagnosed Ph+ CML-CP Patients Who Have Achieved a Sustained Molecular Response (MR4.5)

The ENESTfreedom (Evaluating Nilotinib Efficacy and Safety in clinical Trials-freedom) study (NCT01784068) is an open-label, multicenter, single-arm study, where 215 adult patients with Ph+ CML-CP treated with Tasigna in first-line for ≥ 2 years who achieved MR4.5 as measured with the MolecularMD MRDx® BCR-ABL Test were enrolled to continue Tasigna treatment for an additional 52 weeks (Tasigna consolidation phase).

Of the 215 patients, 190 patients (88.4%) entered the “Treatment-Free Remission” (TFR) phase after achieving a sustained molecular response (MR4.5) during the consolidation phase, defined by the following criteria:

- The 4 last quarterly assessments (taken every 12 weeks) were at least MR4 (BCR-ABL/ABL ≤ 0.01% IS), and maintained for 1 year
- The last assessment being MR4.5 (BCR-ABL/ABL ≤ 0.0032% IS)
- No more than two assessments falling between MR4 and MR4.5 (0.0032% IS < BCR-ABL/ABL ≤ 0.01% IS).

The median age of patients who entered the TFR phase was 55 years, 49.5% were females, and 21.1% of the patients were ≥ 65 years of age. BCR-ABL levels were monitored every 4 weeks during the first 48 weeks of the TFR phase. Monitoring frequency was intensified to every 2 weeks upon the loss of MR4.0. Biweekly monitoring ended at one of the following time points:

- Loss of MMR requiring patient to reinitiate Tasigna treatment
- When the BCR-ABL levels returned to a range between MR4.0 and MR4.5
- When the BCR-ABL levels remained lower than MMR for 4 consecutive measurements (8 weeks from initial loss of MR4.0).

Any patient with loss of MMR during the TFR phase reinitiated Tasigna treatment at 300 mg twice daily or at a reduced dose level of 400 mg once daily if required from the perspective of tolerance, within 5 weeks after the collection date of the blood sample demonstrating loss of MMR. Patients who required reinitiation of Tasigna treatment were monitored for BCR-ABL levels every 4 weeks for the first 24 weeks and then every 12 weeks thereafter in patients who regained MMR.

Efficacy was based on the 96-week analysis data cut-off date, by which time, 91 patients (47.9%) discontinued from the TFR phase due to loss of MMR, and 1 (0.5%), 1 (0.5%), 1 (0.5%) and 3 patients (1.6%) due to death from unknown cause, physician decision, lost to follow-up and subject decision, respectively. Among the 91 patients who discontinued the TFR phase due to loss of MMR, 88 patients restarted Tasigna treatment and 3 patients permanently discontinued from the study.

By the 96-week data cut-off, of the 88 patients who restarted treatment due to loss of MMR in the TFR phase, 87 patients (98.9%) patients regained MMR (one patient discontinued study permanently due to subject decision after 7.1 weeks of retreatment without regaining MMR) and 81 patients (92.0%) regained MR4.5 by the time of the cut-off date. The cumulative rate of MMR and MR4.5 regained at 24 weeks since treatment reinitiation was 97.7% (86/88 patients) and 86.4% (76/88 patients), respectively.

Table 13: Efficacy Results for ENEST Freedom
Patients who entered the treatment free remission (TFR) phase (full analysis Set, N = 190)
 | Patients in TFR phase^1 at the specified time point |  | Loss of MMR^2 by the specified time point
 | % | 95% CI | %
24 weeks | 62.1 | (54.8, 69.0) | 35.8
48 weeks | 51.6 | (44.2, 58.9) | 45.8
96 weeks | 48.9 | (41.6, 56.3) | 47.9
Abbreviation: CI, confidence interval.
^1Patients in MMR at the specified time point in the TFR phase.
^2Based on the time to event (loss of MMR) data during the TFR phase.

Among the 190 patients in the TFR phase, 98 patients had a treatment-free survival (TFS) event (defined as discontinuation from TFR phase due to any reason, loss of MMR, death due to any cause, progression to AP/BC up to the end of TFR phase, or reinitiation of treatment due to any cause in the study) by the 96-week cut-off date.

Figure 1: Kaplan-Meier Estimate of Treatment-Free Survival After Start of TFR (Full Analysis Set ENESTfreedom)

1. For a given time point, the points on the dashed curves represent the 95% confidence limits for the associated KM estimate on the solid curve.
2. By the time of the 96-week data cut-off date, one single patient lost MMR at Week 120, at the time when only 8 patients were considered at risk. This explains the artificial drop at the end of the curve.

14.4 Treatment Discontinuation in Ph+ CML-CP Patients Who Have Achieved a Sustained Molecular Response (MR4.5) on Tasigna Following Prior Imatinib Therapy

The ENESTop (Evaluating Nilotinib Efficacy and Safety in clinical Trials-STop) study (NCT01698905) is an open-label, multicenter, single-arm study, where 163 adult patients with Ph+ CML-CP taking tyrosine kinase inhibitors (TKIs) for ≥ 3 years (imatinib as initial TKI therapy for more than 4 weeks without documented MR4.5 on imatinib at the time of switch to Tasigna, then switched to Tasigna for at least 2 years), and who achieved MR4.5 on Tasigna treatment as measured with the MolecularMD MRDx® BCR-ABL Test were enrolled to continue Tasigna treatment for an additional 52 weeks (Tasigna consolidation phase). Of the 163 patients, 126 patients (77.3%) entered the TFR phase after achieving a sustained molecular response (MR4.5) during the consolidation phase, defined by the following criterion:

- The 4 last quarterly assessments (taken every 12 weeks) showed no confirmed loss of MR4.5 (BCR-ABL/ABL ≤ 0.0032% IS) during 1 year.

The median age of patients who entered the TFR phase was 56 years, 55.6% were females, and 27.8% of the patients were ≥ 65 years of age. The median actual dose intensity during the 52-week Tasigna consolidation phase was 771.8 mg/day with 52.4%, 29.4%, 0.8%, 16.7%, and 0.8% of patients receiving a daily Tasigna dose of 800 mg, 600 mg, 450 mg, 400 mg and 300 mg just before entry into the TFR phase, respectively.

Patients who entered the TFR phase but experienced two consecutive measurements of BCR-ABL/ABL > 0.01% IS were considered having a confirmed loss of MR4.0, triggering reinitiation of Tasigna treatment. Patients with loss of MMR in the TFR phase immediately restarted Tasigna treatment without confirmation. All patients who restarted Tasigna therapy had BCR-ABL transcript levels monitored every 4 weeks for the first 24 weeks, then once every 12 weeks.

Efficacy was based on the 96-week analysis data cut-off date, by which time, 61 patients (48.4%) had discontinued from the TFR phase: 58 patients (46.0%) due to loss of MMR or confirmed loss of MR4.0, 2 patients (1.6%) due to subject/guardian decision and one patient (0.8%) due to pregnancy. Among the 58 patients who discontinued from the TFR phase due to confirmed loss of MR4.0 or loss of MMR, 56 patients restarted Tasigna therapy and 2 patients permanently discontinued from the study.

By the 96-week data cut-off, of the 56 patients who restarted Tasigna treatment due to confirmed loss of MR4.0 or loss of MMR in the TFR phase, 52 patients (92.9%) regained MR4.0 and MR4.5; 4 patients (7.1%) did not regain MR4.0 by the time of the cut-off date. The cumulative rate of MR4 and MR4.5 regained by 48-weeks since treatment reinitiation, was 92.9% (52/56 patients) and 91.1% (51/56 patients), respectively.

Table 14: Efficacy Results for ENESTop
Patients who entered the treatment free remission (TFR) phase (full analysis set, N = 126)
 | Patients in TFR phase^1 at the specified time point |  | Loss of MMR or confirmed loss of MR4^2 by the specified time point
 | % | 95% CI | %
24 weeks | 60.3 | (51.2, 68.9) | 38.9
48 weeks | 57.9 | (48.8, 66.7) | 41.3
96 weeks | 53.2 | (44.1, 62.1) | 43.7
Abbreviation: CI, confidence interval.
^1Patients without loss of MMR or confirmed loss of MR4 by specified time point of TFR phase.
^2Based on the time to event (loss of MMR or confirmed loss of MR4) data during the TFR phase.

Among the 126 patients in the TFR phase, 61 patients (48.4%) had a treatment-free survival (TFS) event (defined as discontinuation from TFR phase due to any reason, loss of MMR, confirmed loss of MR4, death due to any cause, progression to AP/BC up to the end of TFR phase, or reinitiation of treatment due to any cause in the study) on or before the 96-month cut-off date.

Figure 2: Kaplan-Meier Estimate of Treatment-Free Survival after Start of TFR (Full Analysis Set ENESTop)

1. For a given time point, the points on the dashed curves represent the 95% confidence limits for the associated KM estimate on the solid curve.

14.5 Pediatric Patients With Newly Diagnosed Ph+ CML-CP or Resistant or Intolerant Ph+ CML-CP

The safety and efficacy of Tasigna in pediatric patients with Ph+ CML-CP have been investigated in two studies: Study CAMN107A2120 (NCT01077544), an open-label, single-arm, multi-center study that evaluated the pharmacokinetics, safety, and preliminary efficacy of Tasigna in pediatric patients with Ph+ CML resistant or intolerant to imatinib or dasatinib (n = 11), and Study CAMN107A2203 (NCT01844765), an open-label, single-arm, multi-center study evaluating the efficacy and safety of Tasigna in pediatric patients (from 2 to less than 18 years of age) with Ph+ CML-CP resistant or intolerant to imatinib or dasatinib (n = 33) and newly diagnosed Ph+ CML-CP (n = 25). In both studies, patients received Tasigna treatment at a dose of 230 mg/m^2 twice daily, rounded to the nearest 50 mg dose (to a maximum single dose of 400 mg). Data up to 12 cycles was pooled from a total of 69 pediatric patients (from 2 to less than 18 years of age) with either newly diagnosed Ph+ CML-CP (n = 25; 6 children from 2 to less than 12 years and 19 adolescents from 12 to less than 18 years) or imatinib/dasatinib resistant or intolerant Ph+ CML-CP (n = 44; 18 children from 2 to less than 12 years and 26 adolescents from 12 to less than 18 years).

In patients with resistant or intolerant CML, the major molecular response [(MMR); BCR-ABL/ABL ≤ 0.1% IS] rate was 40.9% (18/44, 95% CI: 26.3%, 56.8%) at 12 cycles (28 days per cycle). In patients with newly diagnosed CML, the MMR rate was 60.0% (15/25, 95% CI: 38.7%, 78.9%) at 12 cycles. In patients with resistant or intolerant CML, the cumulative MMR rate was 47.7% (21/44) by Cycle 12. In patients with newly diagnosed CML, the cumulative MMR rate was 64.0% (16/25) by Cycle 12.

Among the 21 patients with resistant or intolerant CML who were in MMR at any time on treatment, the median time to first MMR was 2.8 months (range, 0.0 to 11.3). For the 17 patients with newly diagnosed CML who achieved MMR, the median time to first MMR was 5.6 months (range, 2.7 to 16.6).

Study CAMN107A2203 provided long term data with follow up of approximately 5 years.

By the time of final analysis, the median time on treatment with Tasigna was 51.9 months (range, 1.4 to 61.2 months) for patients with newly diagnosed CML and 60.5 months (range: 0.7 to 63.5 months) for patients with resistant or intolerant CML.

In the patients with resistant or intolerant CML, the major molecular response (MMR; BCR-ABL/ABL ≤0.1% IS) rates were 57.6%, 57.6% by Cycles 24, and 36, respectively. The MMR rate increased to 60.6% by Cycle 48 and was the same until end of study (Cycle 66). In the patients with newly diagnosed CML, the MMR rates were 68.0% by Cycle 24. The MMR rate increased to 76.0% by Cycle 36 and was the same until end of study (Cycle 66).

Among patients with resistant or intolerant CML, 12.1% of patients achieved BCR-ABL/ABL ≤ 0.0032% IS (MR4.5) by Cycle 66. Among patients with newly diagnosed CML, the percentage of patients who achieved MR4.5 was 44%.

None of the 20 patients with resistant or intolerant CML who achieved MMR at any time on treatment by Cycle 66 had confirmed loss of MMR by the end of Cycle 66 or at the time of early discontinuation. Among the 19 patients with newly diagnosed CML who achieved MMR at any time on treatment by the end of Cycle 66, three patients had confirmed loss of MMR. The median durations of MMR could not be estimated in either population as more than half responders did not have a confirmed loss of response by the study end. Range of duration of response was 0.03 to 61 months for resistant or intolerant CML patients and 2.8 to 57.9 months for newly diagnosed CML patients. One patient with resistant or intolerant CML progressed to AP/BC after 10.1 months on treatment.

16 HOW SUPPLIED/STORAGE AND HANDLING

Tasigna (nilotinib) 50 mg capsules are red opaque cap and light yellow opaque body hard gelatin capsules, size 4 with black radial imprint “NVR/ABL.” Tasigna (nilotinib) 150 mg capsules are red opaque hard gelatin capsules, size 1 with black axial imprint “NVR/BCR.” Tasigna (nilotinib) 200 mg capsules are light yellow opaque hard gelatin capsules, size 0 with the red axial imprint “NVR/TKI.” Tasigna 50 mg capsules are supplied in bottles and Tasigna 150 mg and 200 mg capsules are supplied in blister packs.

50 mg

Bottle of 120 capsules………………………………………………………………NDC 0078-0951-66

150 mg

Carton of 4 blister packs of (4x28)…………………………………………………NDC 0078-0592-87

Blisters of 28 capsules………………………………………………………………NDC 0078-0592-51

200 mg

Carton of 4 blister packs of (4x28)…………………………………………………NDC 0078-0526-87

Blisters of 28 capsules………………………………………………………………NDC 0078-0526-51

Tasigna (nilotinib) capsules should be stored at 20°C to 25°C (68°F to 77°F); excursions permitted between 15°C and 30°C (59°F and 86°F) [see USP Controlled Room Temperature].

17 PATIENT COUNSELING INFORMATION

Advise the patient to read the FDA-approved patient labeling (Medication Guide).

A Medication Guide is required for distribution with Tasigna. The complete text of the Medication Guide is reprinted at the end of this document.

Myelosuppression

Advise patients that treatment with Tasigna can cause serious thrombocytopenia, neutropenia, and anemia. Advise patients to seek immediate medical attention if symptoms suggestive of low blood counts occur, such as fever, chills or other signs of infection, unexplained bleeding or bruising, or unexplained weakness or shortness of breath [see Warnings and Precautions (5.1)].

QT Prolongation

Advise patients that Tasigna can cause possibly life-threatening, abnormal heart beat. Advise patients to seek immediate medical attention if symptoms of abnormal heart beat occur, such as feeling light-headed, faint or experiencing an irregular heartbeat [see Warnings and Precautions (5.2)].

Cardiac and Arterial Vascular Occlusive Events

Advise patients that cardiovascular events (including ischemic heart disease, peripheral arterial occlusive disease, and ischemic cerebrovascular events) have been reported. Advise patients to seek immediate medical attention if any symptoms suggestive of a cardiovascular event occur, such as chest or leg pain, numbness or weakness, or problems walking or speaking occur suddenly [see Warnings and Precautions (5.4)].

Pancreatitis and Elevated Serum Lipase

Advise patients that Tasigna can increase the risk of pancreatitis and that patients with a previous history of pancreatitis may be at greater risk. Advise patients to seek immediate medical attention if symptoms suggestive of pancreatitis occur, such as sudden stomach area pain with accompanying nausea and vomiting [see Warnings and Precautions (5.5)].

Hepatotoxicity

Advise patients that Tasigna can increase the risk of hepatotoxicity and that patients with previous history of liver diseases may be at risk. Advise patients to seek immediate medical attention if any symptoms suggestive of hepatotoxicity occur, such as stomach pain, yellow skin and eyes, and dark-colored urine [see Warnings and Precautions (5.6)].

Tumor Lysis Syndrome

Advise patients that Tasigna can cause TLS and to seek immediate medical attention if any symptoms suggestive of TLS occur, such as an abnormal heartbeat or less urine production [see Warnings and Precautions (5.8)].

Hemorrhage

Advise patients that serious hemorrhagic events, including fatal events, have occurred in patients with CML treated with Tasigna. Advise patients to seek immediate medical attention if symptoms suggestive of hemorrhage occur, such as uncontrolled bleeding, changes in eyesight, unconsciousness, or sudden headache or sudden confusion in surroundings [see Warnings and Precautions (5.9)].

Fluid Retention

Advise patients that Tasigna can cause fluid retention and to seek immediate medical attention if any symptoms suggestive of fluid retention, such as shortness of breath, rapid weight gain, or swelling occur [see Warnings and Precautions (5.13)].

Effects on Growth and Development in Pediatric Patients

Inform pediatric patients and their caregivers of the possibility of developing growth abnormalities. Growth retardation has been reported in pediatric patients treated with Tasigna. Therefore, monitor growth and development in pediatric patients [see Warnings and Precautions (5.14)].

Treatment-Free Remission (TFR)

Advise patients that frequent monitoring is required to detect possible loss of remission if TFR is attempted. Advise patients that musculoskeletal symptoms, such as muscle pain, pain in extremity, joint pain, bone pain, or spinal pain, may occur more frequently than before treatment discontinuation [see Warnings and Precautions (5.16)].

Embryo-Fetal Toxicity

Advise pregnant women of the potential risk to a fetus. Advise females of reproductive potential to inform their healthcare provider of a known or suspected pregnancy [see Warnings and Precautions (5.15), Use in Specific Populations (8.1)].

Advise females of reproductive potential to use effective contraception during treatment and for 14 days after receiving the last dose of Tasigna [see Use in Specific Populations (8.3)].

Lactation

Advise women not to breastfeed during treatment with Tasigna and for 14 days after the last dose [see Use in Specific Populations (8.2)].

Drug Interactions

Advise patients that Tasigna and certain other medicines, including over the counter medications or herbal supplements (such as St. John’s Wort), can interact with each other [see Drug Interactions (7)].

Taking Tasigna

Advise patients to take Tasigna doses twice daily approximately 12 hours apart. The capsules should be swallowed whole with water.

Advise patients to take Tasigna on an empty stomach. No food should be consumed for at least 2 hours before the dose is taken and for at least 1 hour after the dose is taken. Patients should not consume grapefruit products and other foods that are known to inhibit CYP3A4 at any time during Tasigna treatment [see Dosage and Administration (2.1), Drug Interactions (7.1, 7.2)].

If the patient missed a dose of Tasigna, the patient should take the next scheduled dose at its regular time. The patient should not take two doses at the same time.

Should patients be unable to swallow capsules, the contents of each capsule may be dispersed in one teaspoon of applesauce and the mixture swallowed immediately (within 15 minutes).

Compliance

Advise patients of the following:

- Continue taking Tasigna every day for as long as their doctor tells them.
- This is a long-term treatment.
- Do not change dose or stop taking Tasigna without first consulting their doctor.
- If a dose is missed, take the next dose as scheduled. Do not take a double dose to make up for the missed capsules.

Distributed by:
Novartis Pharmaceuticals Corporation
East Hanover, New Jersey 07936

© Novartis

T2024-08

Medication Guide
TASIGNA® (ta-sig-na)
(nilotinib)
capsules

What is the most important information I should know about Tasigna?
Tasigna can cause a possible life-threatening heart problem called QTc prolongation. QTc prolongation causes an irregular heartbeat, which may lead to sudden death.
Your healthcare provider should check the electrical activity of your heart with a test called an electrocardiogram (ECG):

• before starting Tasigna
• 7 days after starting Tasigna

• with any dose changes
• regularly during Tasigna treatment

You may lower your chances for having QTc prolongation with Tasigna if you:

- Take Tasigna on an empty stomach:
  - Avoid eating food for at least 2 hours before the dose is taken, and
  - Avoid eating food for at least 1 hour after the dose is taken.
- Avoid grapefruit, grapefruit juice, and any supplement containing grapefruit extract during treatment with Tasigna. Food and grapefruit products increase the amount of Tasigna in your body.
- Avoid taking other medicines or supplements with Tasigna that can also cause QTc prolongation.
- Tasigna can interact with many medicines and supplements and increase your chance for serious and life-threatening side effects.
- Do not take any other medicine during treatment with Tasigna unless your healthcare provider tells you it is okay to do so.
- If you cannot swallow Tasigna capsules whole, you may open the Tasigna capsule and sprinkle the contents of each capsule in 1 teaspoon of applesauce (puréed apple). Swallow the mixture right away (within 15 minutes). For more information, see “How should I take Tasigna?”

Call your healthcare provider right away if you feel lightheaded, faint, or have an irregular heartbeat during treatment with Tasigna. These can be symptoms of QTc prolongation.

What is Tasigna?
Tasigna is a prescription medicine used to treat:

- adults and children who have been newly diagnosed with a certain type of leukemia called Philadelphia chromosome positive chronic myeloid leukemia (Ph+ CML) in chronic phase.
- adults with chronic phase Ph+ CML or accelerated phase Ph+ CML who:
  - are no longer benefiting from other treatments, including imatinib (Gleevec), or
  - have taken other treatments, including imatinib (Gleevec), and cannot tolerate them.
- children with chronic phase Ph+ CML or accelerated phase Ph+ CML who:
  - are no longer benefiting from treatment with a tyrosine-kinase inhibitor medicine, or
  - have taken a tyrosine-kinase inhibitor medicine and cannot tolerate it.

It is not known if Tasigna is safe and effective in children younger than 1 year of age with newly diagnosed, resistant, or intolerant Ph+ CML in chronic phase.

The long-term effects of treating children with Tasigna for a long period of time are not known.

Who should not take Tasigna?
Do not take if you have:

- low levels of potassium or magnesium in your blood
- long QTc syndrome

Before taking Tasigna, tell your healthcare provider about all of your medical conditions, including if you:

- have heart problems
- have had a stroke or other problems due to decreased blood flow to the brain
- have problems with decreased blood flow to your legs
- have irregular heartbeat
- have QTc prolongation or a family history of it
- have liver problems
- have had pancreatitis
- have low blood levels of potassium or magnesium in your blood
- have a severe problem with lactose (milk sugar) or other sugars. Tasigna capsules contain lactose. Most people who have mild or moderate lactose intolerance can take Tasigna.
- have bleeding problems
- had a surgical procedure involving the removal of the entire stomach (total gastrectomy)
- are pregnant or plan to become pregnant. Tasigna can harm your unborn baby. Tell your healthcare provider right away if you are pregnant, or if you become pregnant during treatment with Tasigna.

In females who are able to become pregnant:

- Your healthcare provider should do a pregnancy test before you start treatment with Tasigna.
- Use effective birth control (contraception) during treatment with Tasigna and for 14 days after the last dose.
- are breastfeeding or plan to breastfeed. It is not known if Tasigna passes into your breast milk. Do not breastfeed during treatment and for 14 days after your last dose of Tasigna.

Tell your healthcare provider about all the medicines you take, including prescription and over-the-counter medicines, vitamins and herbal supplements.

If you need to take antacids (medicines to treat heartburn) do not take them at the same time that you take Tasigna. If you take:

- a medicine to block the amount of acid produced in the stomach (H2 blocker): Take these medicines about 10 hours before you take Tasigna, or about 2 hours after you take Tasigna.
- an antacid that contains aluminum hydroxide, magnesium hydroxide, and simethicone to reduce the amount of acid in the stomach: Take these medicines about 2 hours before or about 2 hours after you take Tasigna.

Tasigna can interact with many medicines and supplements and increase your chance for serious and life-threatening side effects. See “What is the most important information I should know about Tasigna?”

How should I take Tasigna?

- Take Tasigna exactly as your healthcare provider tells you to take it.
- Do not change your dose or stop taking Tasigna unless your healthcare provider tells you.
- Tasigna is a long-term treatment.
- Your healthcare provider will tell you how many Tasigna capsules to take and when to take them.
- If your child takes Tasigna, your healthcare provider will change the dose as your child grows.
- Tasigna must be taken on an empty stomach.
  - Avoid eating food for at least 2 hours before the dose is taken, and
  - Avoid eating food for at least 1 hour after the dose is taken.
- Swallow Tasigna capsules whole with water. If you cannot swallow Tasigna capsules whole, tell your healthcare provider.
- If you cannot swallow Tasigna capsules whole:
  - Open the Tasigna capsules and sprinkle the contents in 1 teaspoon of applesauce (puréed apple).
    - Do not use more than 1 teaspoon of applesauce.
    - Only use applesauce. Do not sprinkle Tasigna onto other foods.
  - Swallow the mixture right away (within 15 minutes).
- Do not drink grapefruit juice, eat grapefruit, or take supplements containing grapefruit extract at any time during treatment. See “What is the most important information I should know about Tasigna?”
- If you miss a dose, just take your next dose at your regular time. Do not take 2 doses at the same time to make up for a missed dose.
- If you take too much Tasigna, call your healthcare provider or go to the nearest hospital emergency room right away. Symptoms may include vomiting and drowsiness.
- During treatment with Tasigna your healthcare provider will do tests to check for side effects and to see how well Tasigna is working for you. The tests will check your:
  - heart
  - blood cells (white blood cells, red blood cells, and platelets). Your blood cells should be checked every 2 weeks for the first 2 months and then monthly.
  - electrolytes (potassium, magnesium)
  - pancreas and liver function
  - bone marrow samples

Your healthcare provider may change your dose. Your healthcare provider may have you stop Tasigna for some time or lower your dose if you have side effects with it.

- Your healthcare provider will monitor your CML during treatment with Tasigna to see if you are in a remission. After at least 3 years of treatment with Tasigna, your healthcare provider may do certain tests to determine if you continue to be in remission. Based on your test results, your healthcare provider may decide if you may be eligible to try stopping treatment with Tasigna. This is called Treatment Free Remission (TFR).
- Your healthcare provider will carefully monitor your CML during and after you stop taking Tasigna. Based on your test results, your healthcare provider may need to re-start your Tasigna if your CML is no longer in remission.
- It is important that you are followed by your healthcare provider and undergo frequent monitoring to find out if you need to re-start your Tasigna treatment because you are no longer in TFR. Follow your healthcare provider’s instructions about re-starting Tasigna if you are no longer in TFR.

What are the possible side effects of Tasigna?
Tasigna may cause serious side effects, including:

- See “What is the most important information I should know about Tasigna?”
- Low blood cell counts. Low blood cell counts (red blood cells, white blood cells, and platelets) are common with Tasigna, but can also be severe. Your healthcare provider will check your blood counts regularly during treatment with Tasigna. Call your healthcare provider or get medical help right away if you develop any signs or symptoms of low blood counts, including:
  - fever
  - chills or other signs of infection
  - unexplained bleeding or bruising
  - unexplained weakness
  - shortness of breath
- Decreased blood flow to the leg, heart, or brain. People who have recently been diagnosed with Ph+ CML and take Tasigna may develop decreased blood flow to the leg, the heart, or brain.
  Get medical help right away if you suddenly develop any of the following symptoms:
  - chest pain or discomfort
  - numbness or weakness
  - problems walking or speaking
  - leg pain
  - your leg feels cold
  - change in the skin color of your leg
- Pancreas inflammation (pancreatitis). Tell your healthcare provider right away if you develop any symptoms of pancreatitis, including sudden stomach area pain with nausea and vomiting.
- Liver problems. Tasigna can increase your risk of liver problems. People who have had liver problems in the past may be at risk for getting liver problems with Tasigna. Call your healthcare provider or get medical help right away if you develop any symptoms of liver problems, including:

- stomach area (abdominal) pain

- yellow skin and eyes

- dark-colored urine

- Tumor Lysis Syndrome (TLS). TLS is caused by a fast breakdown of cancer cells. Your healthcare provider may do blood tests to check you for TLS. TLS can cause you to have:
  - kidney failure and the need for dialysis treatment
  - an abnormal heart beat

- Bleeding problems. Serious bleeding problems and death have happened during treatment with Tasigna. Tell your healthcare provider right away if you develop any signs and symptoms of bleeding during treatment with Tasigna.
- Fluid retention. Your body may hold too much fluid (fluid retention). Symptoms of fluid retention include shortness of breath, rapid weight gain, and swelling.
- Abnormal growth or development in children. Effects on growth and development have happened in children with chronic phase Ph+ CML during treatment with Tasigna. Some children and adolescents may have slower than normal growth during treatment with Tasigna.

The most common side effects of Tasigna in adults and children include:

• nausea
• rash
• headache
• tiredness
• itching
• vomiting

• diarrhea
• cough
• constipation
• muscle and joint pain
• runny or stuffy nose, sneezing, sore throat
• fever
• night sweats

Side effects in adult patients attempting treatment free remission:
If you and your healthcare provider decide that you can stop taking Tasigna and try treatment free remission (TFR), you may have more muscle and bone (musculoskeletal) symptoms than before you stopped treatment. Symptoms may include:

• muscle pain
• arm and leg pain
• joint pain

• bone pain
• spine pain

Tell your healthcare provider if you or your child have any side effect that bothers you or does not go away.

These are not all of the possible side effects of Tasigna.

Call your doctor for medical advice about side effects. You may report side effects to FDA at 1-800-FDA-1088.

How should I store Tasigna?

- Store Tasigna at room temperature between 68°F to 77°F (20°C to 25°C).
- Safely throw away medicine that is out of date or no longer needed.

Keep Tasigna and all medicines out of the reach of children.

General information about the safe and effective use of Tasigna.
Medicines are sometimes prescribed for purposes other than those listed in a Medication Guide. Do not use Tasigna for a condition for which it was not prescribed. Do not give Tasigna to other people, even if they have the same symptoms that you have. It may harm them. You can ask your pharmacist or healthcare provider for information about Tasigna that is written for health professionals.

What are the ingredients in Tasigna?
Active ingredient: nilotinib
Inactive ingredients: colloidal silicon dioxide, crospovidone, lactose monohydrate, magnesium stearate and poloxamer 188.
The capsules contain gelatin, iron oxide (red), iron oxide (yellow), iron oxide (black), and titanium dioxide.
Distributed by: Novartis Pharmaceuticals Corporation, East Hanover, New Jersey 07936
© Novartis
For more information, go to www.Tasigna.com or call 1-888-669-6682.

This Medication Guide has been approved by the U.S. Food and Drug Administration.

Revised: February 2025

T2025-05

PRINCIPAL DISPLAY PANEL

NDC 0078-0951-66

120 capsules

Rx Only

Tasigna®
(nilotinib) capsules

50 mg

Dispense with Medication Guide

NOVARTIS

PRINCIPAL DISPLAY PANEL

NDC 0078-0592-87

Tasigna®
(nilotinib) capsules

150 mg
per capsule

DISPENSE WITH MEDICATION GUIDE
ATTACHED OR PROVIDED SEPARATELY.

NOVARTIS

PRINCIPAL DISPLAY PANEL

NDC 0078-0526-87

Tasigna®
(nilotinib) capsules

200 mg
per capsule

DISPENSE WITH MEDICATION GUIDE
ATTACHED OR PROVIDED SEPARATELY.

NOVARTIS